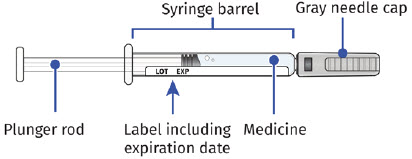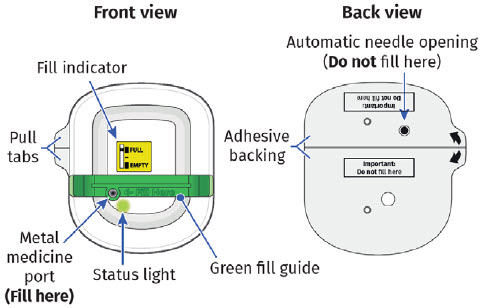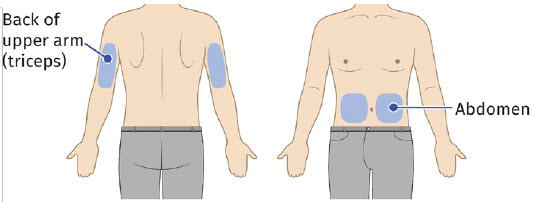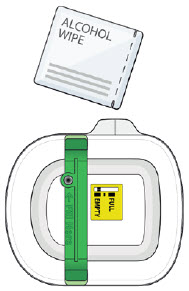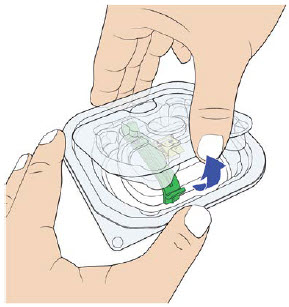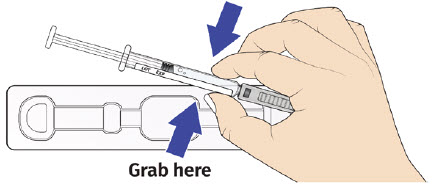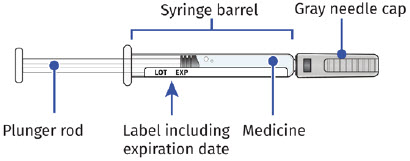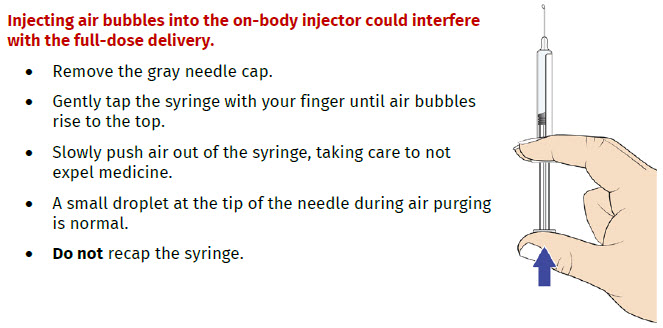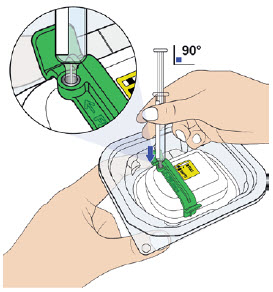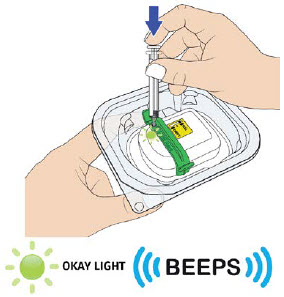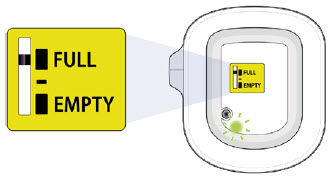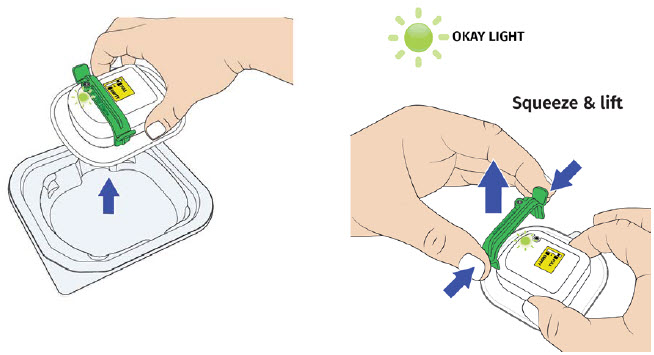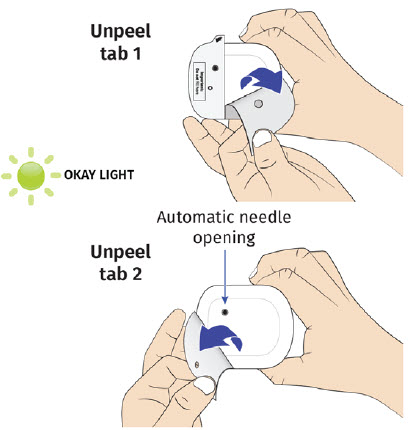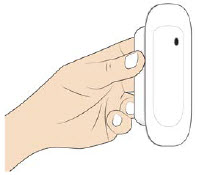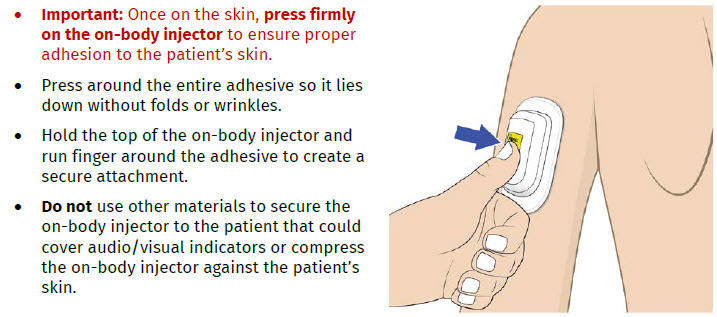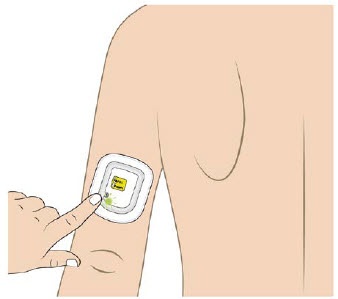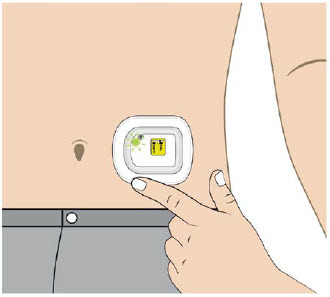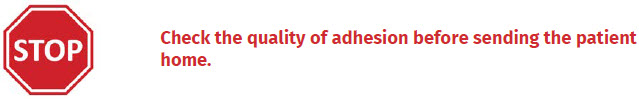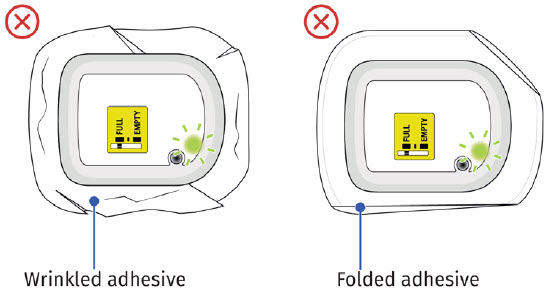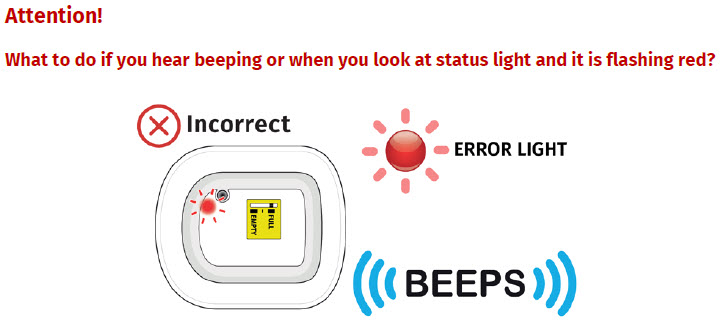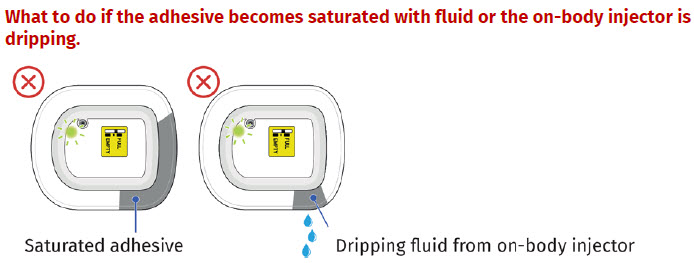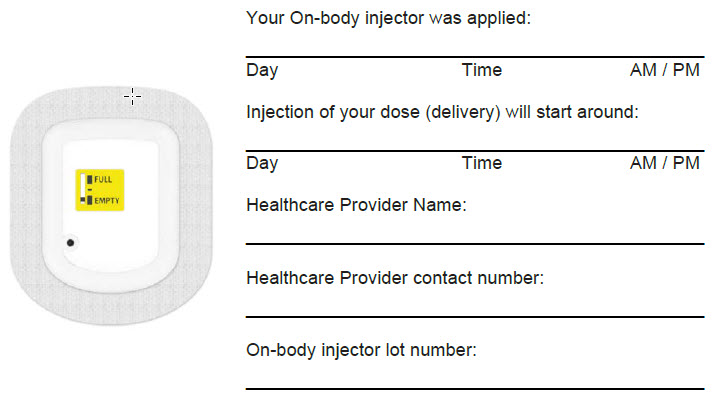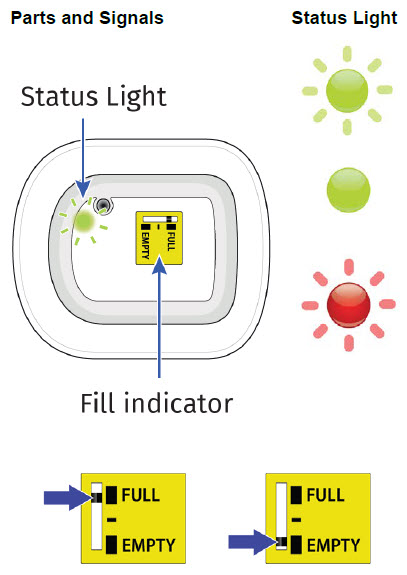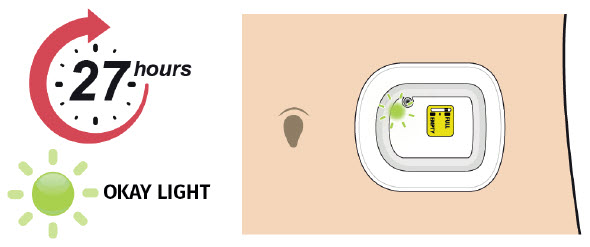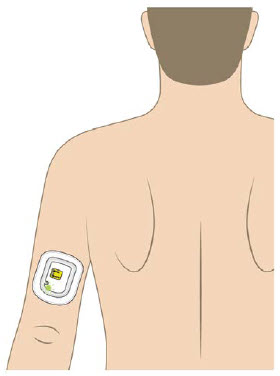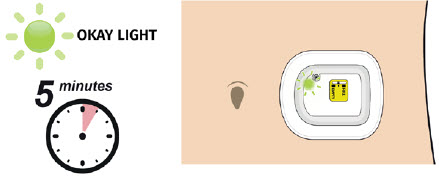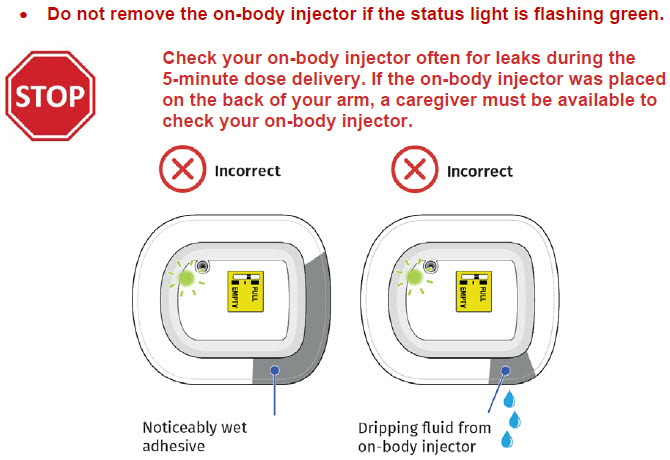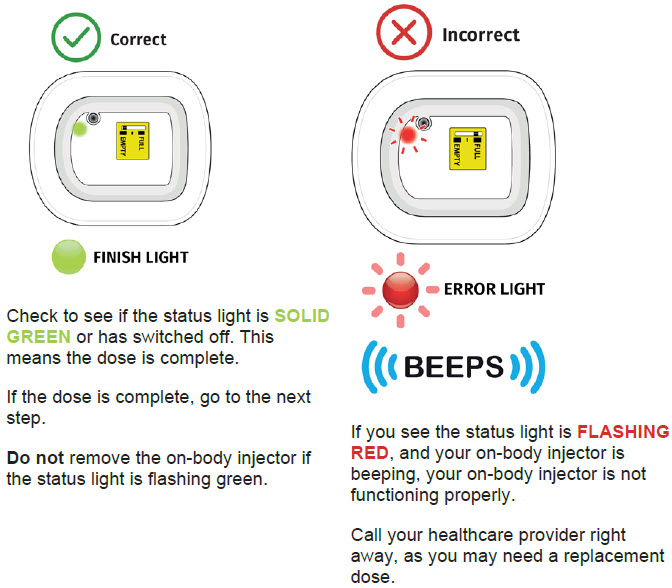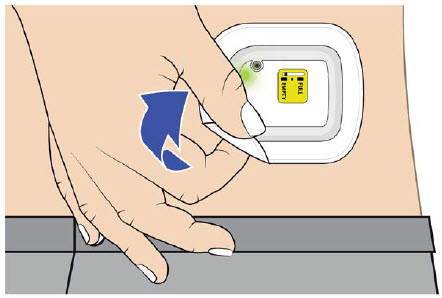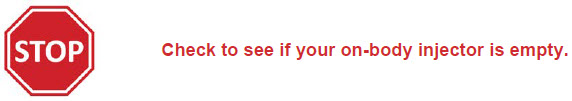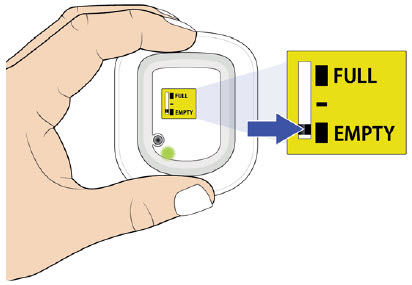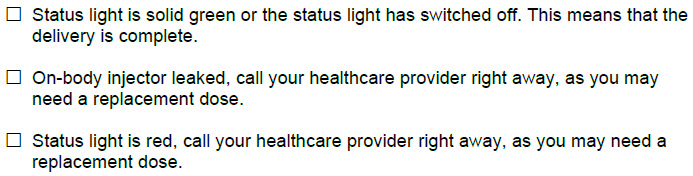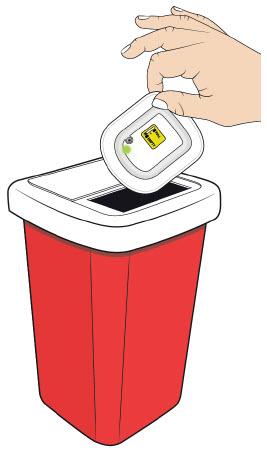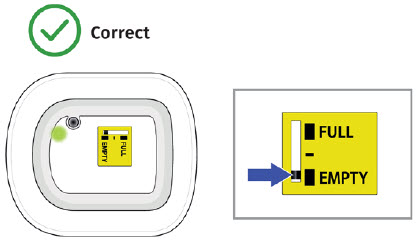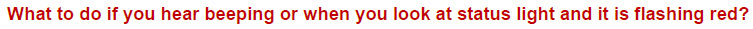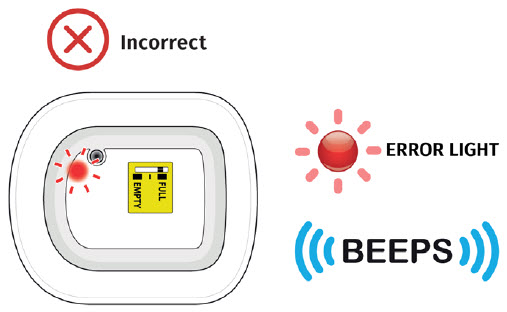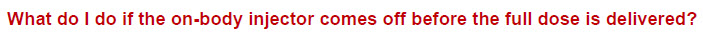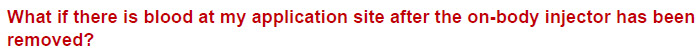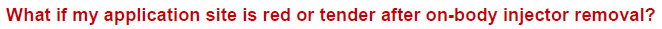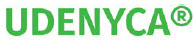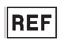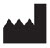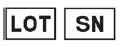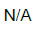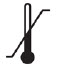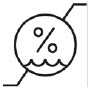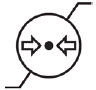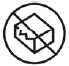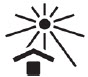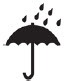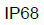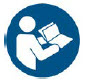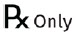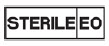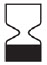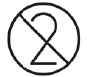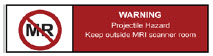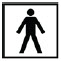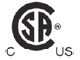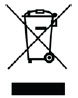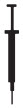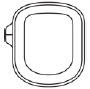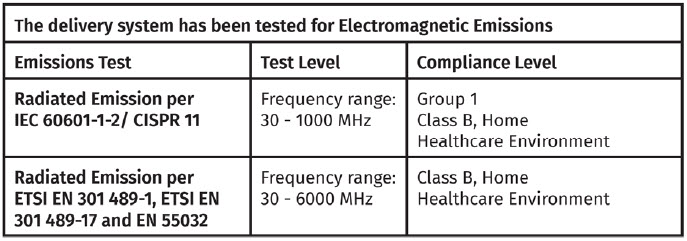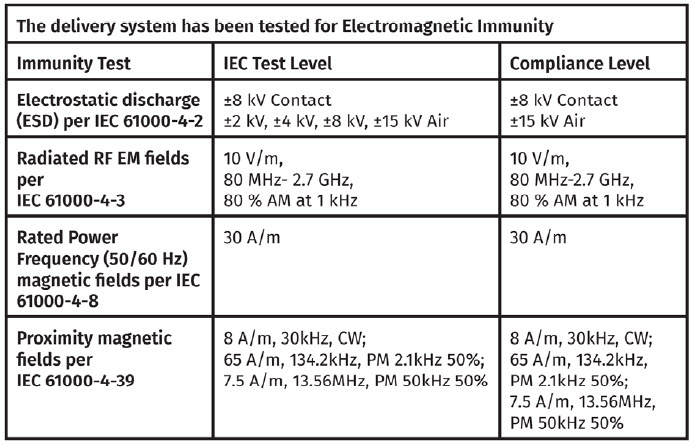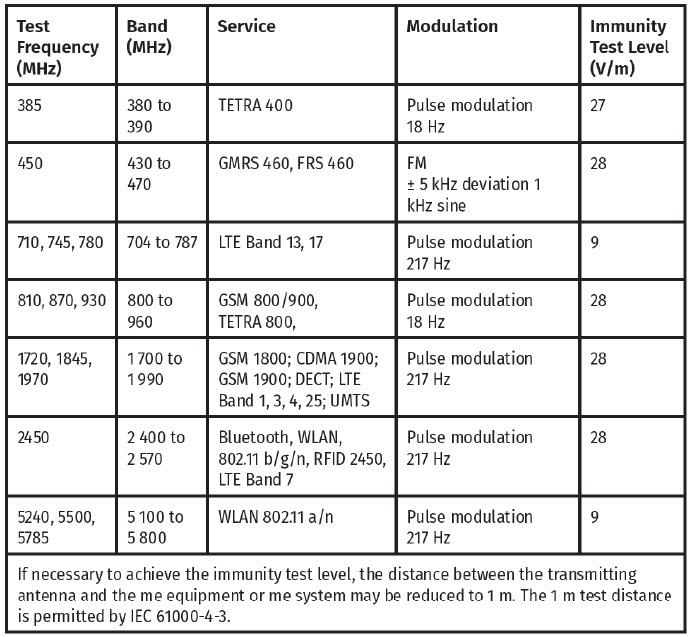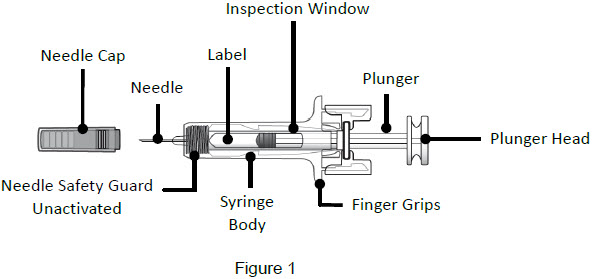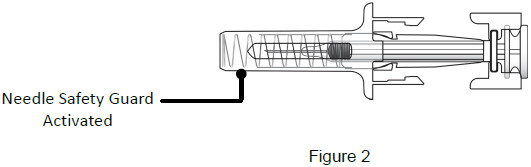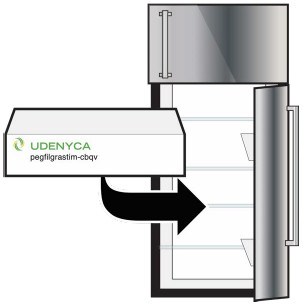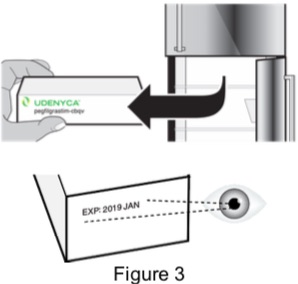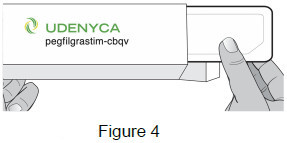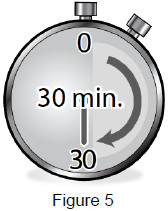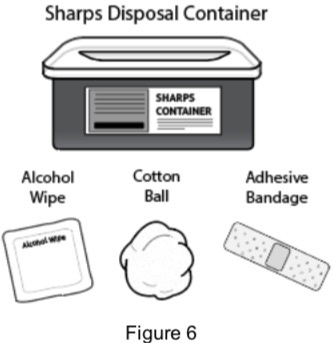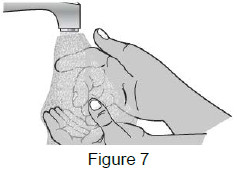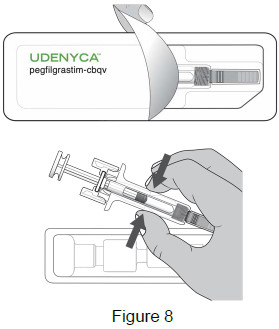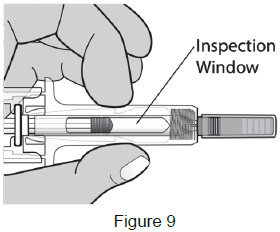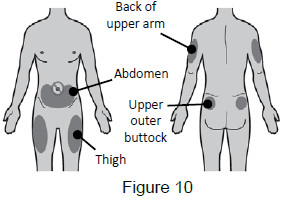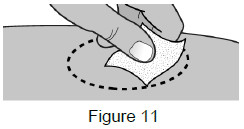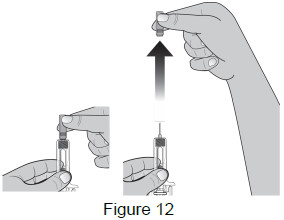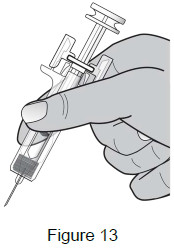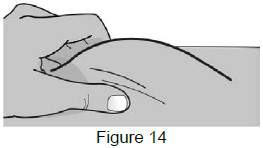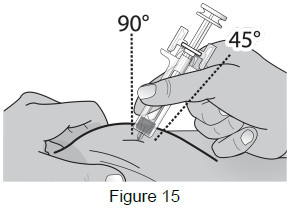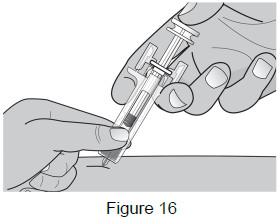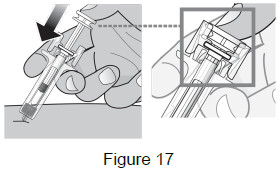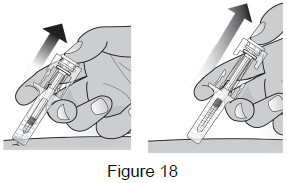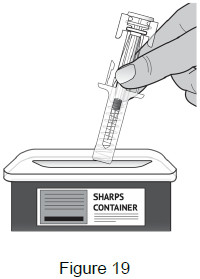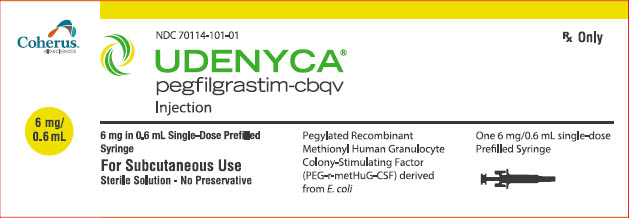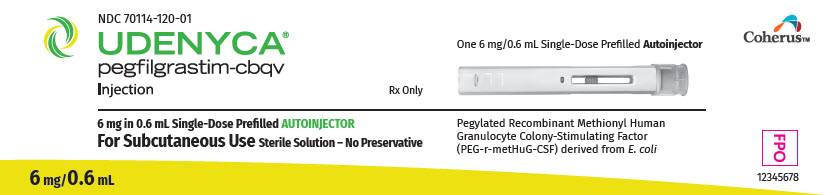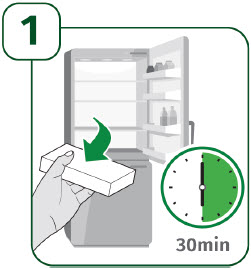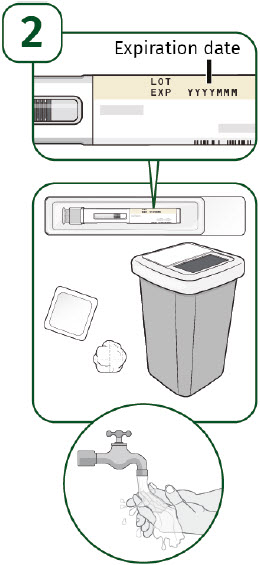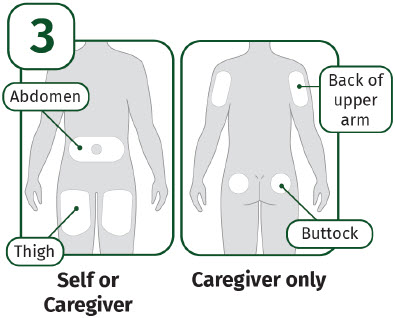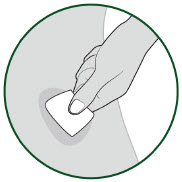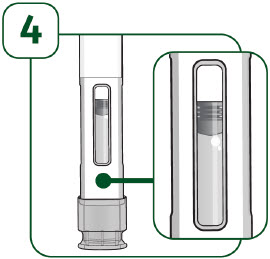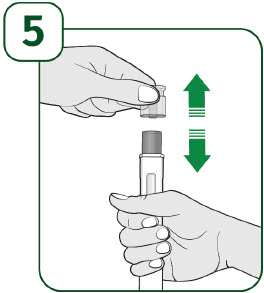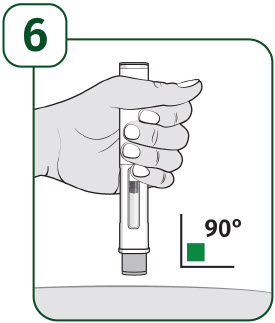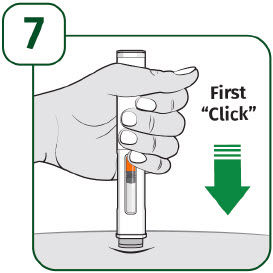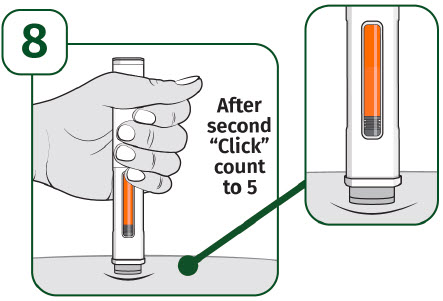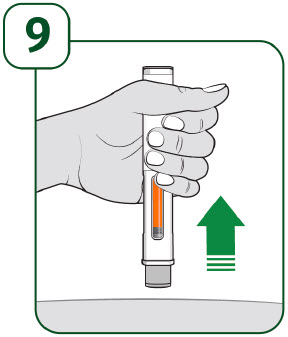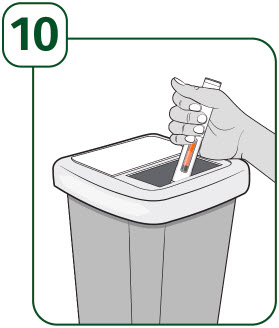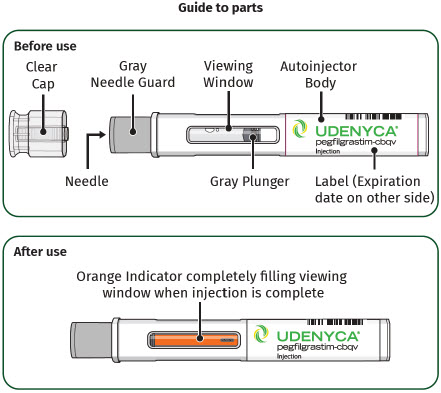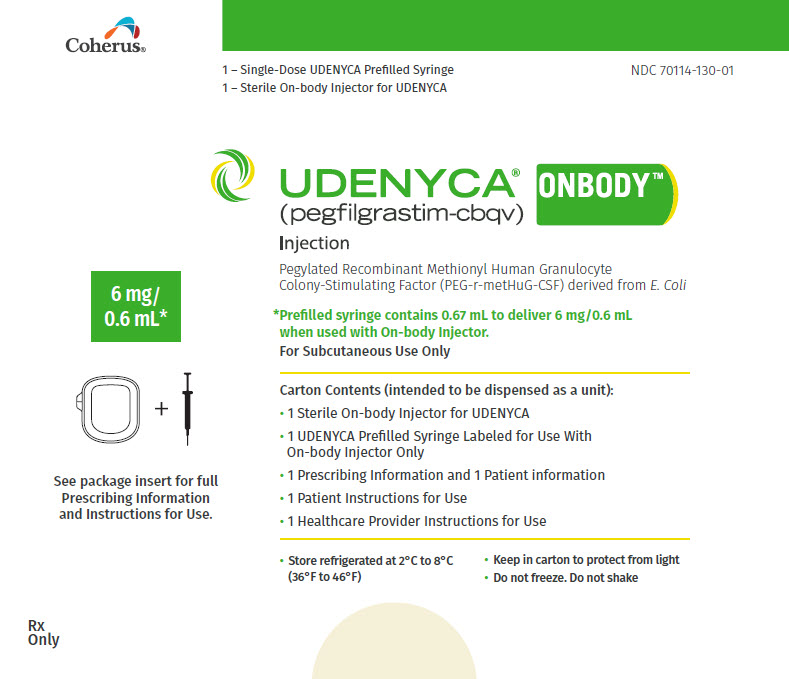 DRUG LABEL: UDENYCA
NDC: 70114-101 | Form: INJECTION, SOLUTION
Manufacturer: Coherus Oncology, Inc.
Category: prescription | Type: HUMAN PRESCRIPTION DRUG LABEL
Date: 20250814

ACTIVE INGREDIENTS: PEGFILGRASTIM 6 mg/0.6 mL
INACTIVE INGREDIENTS: ACETATE ION; POLYSORBATE 20; SODIUM; SORBITOL; WATER

HIGHLIGHTS OF PRESCRIBING INFORMATION

These highlights do not include all the information needed to use UDENYCA safely and effectively. See full prescribing information for UDENYCA.
UDENYCA® (pegfilgrastim-cbqv) injection, for subcutaneous use
INITIAL U.S. APPROVAL: 2018
UDENYCA (pegfilgrastim-cbqv) is biosimilar [Biosimilar means that the biological product is approved based on data demonstrating that it is highly similar to an FDA-approved biological product, known as a reference product, and that there are no clinically meaningful differences between the biosimilar product and the reference product. Biosimilarity of UDENYCA has been demonstrated for the condition(s) of use (e.g. indication(s), dosing regimen(s), strength(s), dosage form(s), and route(s) of administration) described in its Full Prescribing Information.] to NEULASTA (pegfilgrastim).

RECENT MAJOR CHANGES

Dosage and Administration (2.2) and (2.3) 12/2023

1 INDICATIONS AND USAGE

UDENYCA is a leukocyte growth factor indicated to

- Decrease the incidence of infection, as manifested by febrile neutropenia, in patients with non-myeloid malignancies receiving myelosuppressive anti-cancer drugs associated with a clinically significant incidence of febrile neutropenia. (1.1)
- Increase survival in patients acutely exposed to myelosuppressive doses of radiation (Hematopoietic Subsyndrome of Acute Radiation Syndrome). (1.2)

Limitations of Use

UDENYCA is not indicated for the mobilization of peripheral blood progenitor cells for hematopoietic stem cell transplantation.

2 DOSAGE AND ADMINISTRATION

- Patients with cancer receiving myelosuppressive chemotherapy
  - 6 mg administered subcutaneously once per chemotherapy cycle. (2.1)
  - Do not administer between 14 days before and 24 hours after administration of cytotoxic chemotherapy. (2.1)
  - Use weight based dosing for pediatric patients weighing less than 45 kg; refer to Table 1. (2.3)

- Patients acutely exposed to myelosuppressive doses of radiation
  - Two doses, 6 mg each, administered subcutaneously one week apart. Administer the first dose as soon as possible after suspected or confirmed exposure to myelosuppressive doses of radiation, and a second dose one week after. (2.2)
  - Use weight based dosing for pediatric patients weighing less than 45 kg; refer to Table 1. (2.3)

3 DOSAGE FORMS AND STRENGTHS

Injection:

- 6 mg/0.6 mL in a single-dose prefilled syringe for manual use only. (3)
- 6 mg/0.6 mL in a single-dose prefilled autoinjector. (3)
- 6 mg/0.6 mL in a single-dose prefilled syringe co-packaged with the on-body injector for UDENYCA. (3)

4 CONTRAINDICATIONS

Patients with a history of serious allergic reaction to human granulocyte colony-stimulating factors such as pegfilgrastim products or filgrastim products. (4)

5 WARNINGS AND PRECAUTIONS

- Fatal splenic rupture: Evaluate patients who report left upper abdominal or shoulder pain for an enlarged spleen or splenic rupture (5.1)
- Acute respiratory distress syndrome (ARDS): Evaluate patients who develop fever, lung infiltrates, or respiratory distress. Discontinue UDENYCA in patients with ARDS. (5.2)
- Serious allergic reactions, including anaphylaxis: Permanently discontinue UDENYCA in patients with serious allergic reactions. (5.3)
- The on-body injector for UDENYCA uses acrylic adhesives. For patients who have reactions to acrylic adhesives, use of this product may result in a significant reaction. (5.4)
- Fatal sickle cell crises: Discontinue UDENYCA if sickle cell crisis occurs. (5.5)
- Glomerulonephritis: Evaluate and consider dose-reduction or interruption of UDENYCA if causality is likely. (5.6)
- Thrombocytopenia: Monitor platelet count (5.8)
- Myelodysplastic Syndrome (MDS) and Acute Myeloid Leukemia (AML): Monitor patients with breast and lung cancer using UDENYCA in conjunction with chemotherapy and/or radiotherapy for signs and symptoms of MDS/AML. (5.11)
- Potential device failures: Instruct patients to notify their healthcare provider if they suspect the on-body injector may not have performed as intended. (5.12)

6 ADVERSE REACTIONS

Most common adverse reactions (≥ 5% difference in incidence compared to placebo) are bone pain and pain in extremity. (6.1)

To report SUSPECTED ADVERSE REACTIONS, contact Coherus BioSciences at 1-800-4UDENYCA (1-800-483-3692) or FDA at 1-800-FDA-1088 (1-800-332-1088) or www.fda.gov/medwatch

FULL PRESCRIBING INFORMATION

1 INDICATIONS AND USAGE

1.1 Patients with Cancer Receiving Myelosuppressive Chemotherapy

UDENYCA is indicated to decrease the incidence of infection, as manifested by febrile neutropenia, in patients with non-myeloid malignancies receiving myelosuppressive anti-cancer drugs associated with a clinically significant incidence of febrile neutropenia [see Clinical Studies (14.1)].

Limitations of Use

UDENYCA is not indicated for the mobilization of peripheral blood progenitor cells for hematopoietic stem cell transplantation.

1.2 Patients with Hematopoietic Subsyndrome of Acute Radiation Syndrome

UDENYCA is indicated to increase survival in patients acutely exposed to myelosuppressive doses of radiation [see Dosage and Administration (2.2) and Clinical Studies (14.2)].

2 DOSAGE AND ADMINISTRATION

2.1 Patients with Cancer Receiving Myelosuppressive Chemotherapy

The recommended dosage of UDENYCA is a single subcutaneous injection of 6 mg administered once per chemotherapy cycle. For dosing in pediatric patients weighing less than 45 kg, refer to Table 1. Do not administer UDENYCA between 14 days before and 24 hours after administration of cytotoxic chemotherapy.

2.2 Patients with Hematopoietic Subsyndrome of Acute Radiation Syndrome

The recommended dose of UDENYCA is two doses, 6 mg each, administered subcutaneously one week apart. For dosing in pediatric patients weighing less than 45 kg, refer to Table 1. Administer the first dose as soon as possible after suspected or confirmed exposure to radiation levels greater than 2 gray (Gy). Administer the second dose one week after the first dose.

Obtain a baseline complete blood count (CBC). Do not delay administration of UDENYCA if a CBC is not readily available. Estimate a patient’s absorbed radiation dose (i.e., level of radiation exposure) based on information from public health authorities, biodosimetry if available, or clinical findings such as time to onset of vomiting or lymphocyte depletion kinetics.

2.3 Administration

UDENYCA is administered subcutaneously via a single-dose prefilled autoinjector, a single-dose prefilled syringe for manual use or for use with the on-body injector (OBI) for UDENYCA, which is co-packaged with a single dose prefilled syringe for OBI. Use of the OBI for UDENYCA is not recommended for patients with Hematopoietic Subsyndrome of Acute Radiation Syndrome. Use of the OBI has not been studied in pediatric patients.

Prior to use‚ remove the carton from the refrigerator and allow UDENYCA to reach room temperature for a minimum of 30 minutes. Discard any UDENYCA left at room temperature for greater than 48 hours.

Parenteral drug products should be inspected visually for particulate matter and discoloration prior to administration, whenever solution and container permit. Do not administer UDENYCA if discoloration or particulates are observed.

The needle cap on the prefilled syringe and prefilled autoinjector is not made with natural rubber latex.

Pediatric Patients Weighing Less than 45 kg

The UDENYCA prefilled syringe is not designed to allow for direct administration of doses less than 0.6 mL (6 mg). The syringe does not bear graduation marks which are necessary to accurately measure doses of UDENYCA less than 0.6 mL (6 mg) for direct administration to patients. Thus, the direct administration to patients requiring dosing of less than 0.6 mL (6 mg) is not recommended due to the potential for dosing errors. Refer to Table 1.

Table 1. Dosing of UDENYCA for pediatric patients weighing less than 45 kg
Body Weight | UDENYCA Dose | Volume to Administer
Less than 10 kg [For pediatric patients weighing less than 10 kg, administer 0.1 mg/kg (0.01 mL/kg) of UDENYCA] | See below | See below
10 - 20 kg | 1.5 mg | 0.15 mL
21 - 30 kg | 2.5 mg | 0.25 mL
31 - 44 kg | 4 mg | 0.4 mL

The UDENYCA prefilled autoinjector is not suitable for use in pediatric patients weighing less than 45 kg. The UDENYCA prefilled autoinjector delivers the entire contents (6 mg in 0.6 mL) in a single injection and is not adjustable.

2.4 Advice to Give to Patients or Caregivers Regarding Administration via the Prefilled Autoinjector

Only adults can self-administer UDENYCA with the prefilled autoinjector. If subcutaneous injections can be given at home, refer the patient or caregiver to the dose delivery information provided in the Instructions for Use. Provide training to patients or caregivers to ensure they understand how to administer UDENYCA via the prefilled autoinjector. Ensure patients or caregivers understand how to identify that a full dose has been administered by listening for the second 'click' and checking that the 'Orange Indicator' completely blocks the viewing window. Instruct patients or caregivers using the prefilled autoinjector to notify their healthcare provider immediately in order to determine the need for a replacement dose of UDENYCA if they suspect that the full dose may not have been administered.

2.5 Special Healthcare Provider Instructions for the On-body Injector for UDENYCA

A healthcare provider must fill the on-body injector (OBI) with UDENYCA using the prefilled syringe and then apply the OBI for UDENYCA to the patient's skin (abdomen or back of arm). The back of the arm may only be used if there is a caregiver available to monitor the status of the OBI for UDENYCA. Approximately 27 hours after the OBI for UDENYCA is applied to the patient's skin, UDENYCA will be delivered over approximately 5 minutes. A healthcare provider may initiate administration with the OBI for UDENYCA on the same day as the administration of cytotoxic chemotherapy, as long as the OBI for UDENYCA delivers UDENYCA no less than 24 hours after administration of cytotoxic chemotherapy.

The prefilled syringe co-packaged in UDENYCA ONBODY must only be used with the OBI for UDENYCA. The prefilled syringe contains additional solution to compensate for liquid loss during filling of the OBI and delivery through the OBI for UDENYCA. If the prefilled syringe co-packaged in UDENYCA ONBODY is used for manual subcutaneous injection, the patient will receive an overdose. If the single-dose prefilled syringe for manual use is used with the OBI for UDENYCA, the patient may receive less than the recommended dose.

Do not use the OBI for UDENYCA to deliver any other drug product except the UDENYCA prefilled syringe co-packaged with the OBI for UDENYCA.

The OBI for UDENYCA should be applied to intact, non-irritated skin on the arm or abdomen.

A missed dose could occur due to an OBI for UDENYCA failure or leakage. If the patient misses a dose, a new dose should be administered by single-dose prefilled syringe for manual use, as soon as possible after detection.

Refer to the Healthcare Provider Instructions for Use for the OBI for UDENYCA for full administration information.

2.6 Advice to give to Patients Regarding Administration via the On-body Injector for UDENYCA

Advise patients to avoid activities such as traveling, driving, or operating heavy machinery during hours 26-29 following application of the on-body injector (OBI) for UDENYCA (this includes the 5-minute delivery period plus an hour post-delivery). Patients should have a caregiver nearby for the first use.

Refer the patient to the dose delivery information written on the Patient Instructions for Use. Provide training to patients to ensure they understand when the dose delivery of UDENYCA will begin and how to monitor the OBI for UDENYCA for completed delivery. Ensure patients understand how to identify signs of malfunction of OBI for UDENYCA [see Warnings and Precautions (5.12) and Patient Counseling Information (17)]. Instruct patients using the OBI to notify their healthcare professional immediately in order to determine the need for a replacement dose of UDENYCA if they suspect that the device may not have performed as intended [see Warnings and Precautions (5.12)].

3 DOSAGE FORMS AND STRENGTHS

UDENYCA is a clear, colorless, preservative free solution available as:

- Injection: 6 mg/0.6 mL in a single-dose prefilled syringe for manual use only.
- Injection: 6 mg/0.6 mL in a single-dose prefilled autoinjector.
- Injection: 6mg/0.6 mL in a single-dose prefilled syringe co-packaged with the on-body injector (OBI) for UDENYCA (UDENYCA ONBODY).

4 CONTRAINDICATIONS

UDENYCA is contraindicated in patients with a history of serious allergic reactions to pegfilgrastim products or filgrastim products. Reactions have included anaphylaxis [see Warnings and Precautions (5.3)].

5 WARNINGS AND PRECAUTIONS

5.1 Splenic Rupture

Splenic rupture, including fatal cases, can occur following the administration of pegfilgrastim products. Evaluate for an enlarged spleen or splenic rupture in patients who report left upper abdominal or shoulder pain after receiving UDENYCA.

5.2 Acute Respiratory Distress Syndrome

Acute respiratory distress syndrome (ARDS) can occur in patients receiving pegfilgrastim products. Evaluate patients who develop fever and lung infiltrates or respiratory distress after receiving UDENYCA for ARDS. Discontinue UDENYCA in patients with ARDS.

5.3 Serious Allergic Reactions

Serious allergic reactions, including anaphylaxis, can occur in patients receiving pegfilgrastim products. The majority of reported events occurred upon initial exposure. Allergic reactions, including anaphylaxis, can recur within days after the discontinuation of initial anti-allergic treatment. Permanently discontinue UDENYCA in patients with serious allergic reactions. Do not administer UDENYCA to patients with a history of serious allergic reactions to pegfilgrastim products or filgrastim products.

5.4 Allergies to Acrylics

The on-body injector (OBI) for UDENYCA uses acrylic adhesive. For patients who have reactions to acrylic adhesives, use of this product may result in a significant reaction.

5.5 Use in Patients with Sickle Cell Disorders

Severe and sometimes fatal sickle cell crises can occur in patients with sickle cell disorders receiving pegfilgrastim products. Discontinue UDENYCA if sickle cell crisis occurs.

5.6 Glomerulonephritis

Glomerulonephritis has occurred in patients receiving pegfilgrastim products. The diagnoses were based upon azotemia, hematuria (microscopic and macroscopic), proteinuria, and renal biopsy. Generally, events of glomerulonephritis resolved after dose reduction or discontinuation of pegfilgrastim products. If glomerulonephritis is suspected, evaluate for cause. If causality is likely, consider dose-reduction or interruption of UDENYCA.

5.7 Leukocytosis

White blood cell (WBC) counts of 100 x 10^9/L or greater have been observed in patients receiving pegfilgrastim products. Monitoring of complete blood count (CBC) during UDENYCA therapy is recommended.

5.8 Thrombocytopenia

Thrombocytopenia has been reported in patients receiving pegfilgrastim products. Monitor platelet counts.

5.9 Capillary Leak Syndrome

Capillary leak syndrome has been reported after G-CSF administration, including pegfilgrastim products, and is characterized by hypotension, hypoalbuminemia, edema, and hemoconcentration. Episodes vary in frequency, severity and may be life-threatening if treatment is delayed. Patients who develop symptoms of capillary leak syndrome should be closely monitored and receive standard symptomatic treatment, which may include a need for intensive care.

5.10 Potential for Tumor Growth Stimulatory Effects on Malignant Cells

The granulocyte colony-stimulating factor (G-CSF) receptor through which pegfilgrastim products and filgrastim products act has been found on tumor cell lines. The possibility that pegfilgrastim products act as a growth factor for any tumor type, including myeloid malignancies and myelodysplasia, diseases for which pegfilgrastim products are not approved, cannot be excluded.

5.11 Myelodysplastic Syndrome (MDS) and Acute Myeloid Leukemia (AML) in Patients with Breast and Lung Cancer

MDS and AML have been associated with the use of pegfilgrastim products in conjunction with chemotherapy and/or radiotherapy in patients with breast and lung cancer. Monitor patients for signs and symptoms of MDS/AML in these settings.

5.12 Potential Device failures

Missed or partial doses have been reported in patients receiving UDENYCA via the on-body injector (OBI) due to the device not performing as intended. In the event of a missed or partial dose, patients may be at increased risk of events such as neutropenia, febrile neutropenia and/or infection than if the dose had been correctly delivered.

Instruct patients using the OBI to notify their healthcare professional immediately in order to determine the need for a replacement dose of UDENYCA if they suspect that the device may not have performed as intended.

5.13 Aortitis

Aortitis has been reported in patients receiving pegfilgrastim products. It may occur as early as the first week after start of therapy. Manifestations may include generalized signs and symptoms such as fever, abdominal pain, malaise, back pain, and increased inflammatory markers (e.g., c-reactive protein and white blood cell count). Consider aortitis in patients who develop these signs and symptoms without known etiology. Discontinue UDENYCA if aortitis is suspected.

5.14 Nuclear Imaging

Increased hematopoietic activity of the bone marrow in response to growth factor therapy has been associated with transient positive bone imaging changes. This should be considered when interpreting bone imaging results.

6 ADVERSE REACTIONS

The following clinically significant adverse reactions are discussed in greater detail in other sections of the labeling:

- Splenic Rupture [see Warnings and Precautions (5.1)]
- Acute Respiratory Distress Syndrome [see Warnings and Precautions (5.2)]
- Serious Allergic Reactions [see Warnings and Precautions (5.3)]
- Allergies to Acrylics [see Warnings and Precautions (5.4)]
- Use in Patients with Sickle Cell Disorders [see Warnings and Precautions (5.5)]
- Glomerulonephritis [see Warnings and Precautions (5.6)]
- Leukocytosis [see Warnings and Precautions (5.7)]
- Thrombocytopenia [see Warnings and Precautions (5.8)]
- Capillary Leak Syndrome [see Warnings and Precautions (5.9)]
- Potential for Tumor Growth Stimulatory Effects on Malignant Cells [see Warnings and Precautions (5.10)]
- Myelodysplastic syndrome [see Warnings and Precautions (5.11)]
- Acute myeloid leukemia [see Warnings and Precautions (5.11)]
- Aortitis [see Warnings and Precautions (5.13)]

6.1 Clinical Trials Experience

Because clinical trials are conducted under widely varying conditions, adverse reaction rates observed in the clinical trials of a drug cannot be directly compared with rates in the clinical trials of another drug and may not reflect the rates observed in clinical practice.

Pegfilgrastim clinical trials safety data are based upon 932 patients receiving pegfilgrastim in seven randomized clinical trials. The population was 21 to 88 years of age and 92% female. The ethnicity was 75% Caucasian, 18% Hispanic, 5% Black, and 1% Asian. Patients with breast (n = 823), lung and thoracic tumors (n = 53) and lymphoma (n = 56) received pegfilgrastim after nonmyeloablative cytotoxic chemotherapy. Most patients received a single 100 mcg/kg (n = 259) or a single 6 mg (n = 546) dose per chemotherapy cycle over 4 cycles.

The following adverse reaction data in Table 2 are from a randomized, double-blind, placebo-controlled study in patients with metastatic or non-metastatic breast cancer receiving docetaxel 100 mg/m^2 every 21 days (Study 3). A total of 928 patients were randomized to receive either 6 mg pegfilgrastim (n = 467) or placebo (n = 461). The patients were 21 to 88 years of age and 99% female. The ethnicity was 66% Caucasian, 31% Hispanic, 2% Black, and <1% Asian, Native American or other.

The most common adverse reactions occurring in ≥ 5% of patients and with a between-group difference of ≥ 5% higher in the pegfilgrastim arm in placebo controlled clinical trials are bone pain and pain in extremity.

Table 2. Adverse Reactions with ≥ 5% Higher Incidence in pegfilgrastim Patients Compared to Placebo in Study 3
Body System Adverse Reaction | Placebo (N = 461) | pegfilgrastim 6 mg SC on Day 2 (N = 467)
Musculoskeletal and connective tissue disorders
Bone pain | 26% | 31%
Pain in extremity | 4% | 9%

Leukocytosis

In clinical studies, leukocytosis (WBC counts > 100 x 10^9/L was observed in less than 1% of 932 patients with non-myeloid malignancies receiving pegfilgrastim. No complications attributable to leukocytosis were reported in clinical studies.

6.2 Immunogenicity

The observed incidence of anti-drug antibodies is highly dependent on the sensitivity and specificity of the assay. Differences in assay methods preclude meaningful comparisons of the incidence of anti-drug antibodies in the studies described below with the incidence of anti-drug antibodies in other studies, including those of pegfilgrastim or of other pegfilgrastim products.

Binding antibodies to pegfilgrastim were detected using a BIAcore assay. The approximate limit of detection for this assay is 500 ng/mL. Pre-existing binding antibodies were detected in approximately 6% (51/849) of patients with metastatic breast cancer. Four of 521 pegfilgrastim-treated subjects who were negative at baseline developed binding antibodies to pegfilgrastim following treatment. None of these 4 patients had evidence of neutralizing antibodies detected using a cell-based bioassay.

6.3 Postmarketing Experience

The following adverse reactions have been identified during post approval use of pegfilgrastim products. Because these reactions are reported voluntarily from a population of uncertain size, it is not always possible to reliably estimate their frequency or establish a causal relationship to drug exposure.

- Splenic rupture and splenomegaly (enlarged spleen) [see Warnings and Precautions (5.1)]
- Acute respiratory distress syndrome (ARDS) [see Warnings and Precautions (5.2)]
- Allergic reactions/hypersensitivity, including anaphylaxis, skin rash, urticaria, generalized erythema and flushing [see Warnings and Precautions (5.3)]
- Sickle cell crisis [see Warnings and Precautions (5.5)]
- Glomerulonephritis [see Warnings and Precautions (5.6)]
- Leukocytosis [see Warnings and Precautions (5.7)]
- Thrombocytopenia [see Warnings and Precautions (5.8)]
- Capillary leak syndrome [see Warnings and Precautions (5.9)]
- Injection site reactions
- Sweet’s syndrome (acute febrile neutrophilic dermatosis), cutaneous vasculitis
- Application site reactions (including events such as application site hemorrhage, application site pain, application site discomfort, application site bruise, and application site erythema) have been reported with the use of the on-body-injector for UDENYCA.
- Contact dermatitis and local skin reactions such as rash, pruritus, and urticaria have been reported with the use of the on-body-injector for UDENYCA, possibly indicating a hypersensitivity reaction to the adhesive.
- Myelodysplastic syndrome (MDS) and acute myeloid leukemia (AML) in patients with breast and lung cancer receiving chemotherapy and/or radiotherapy [see Warnings and Precautions (5.11)]
- Aortitis [see Warnings and Precautions (5.13)]
- Alveolar hemorrhage

8 USE IN SPECIFIC POPULATIONS

8.1 Pregnancy

Risk Summary

Although available data with UDENYCA or pegfilgrastim product use in pregnant women are insufficient to establish whether there is a drug associated risk of major birth defects, miscarriage, or adverse maternal or fetal outcomes, there are available data from published studies in pregnant women exposed to filgrastim products. These studies have not established an association of filgrastim product use during pregnancy with major birth defects, miscarriage, or adverse maternal or fetal outcomes.

In animal studies, no evidence of reproductive/developmental toxicity occurred in the offspring of pregnant rats that received cumulative doses of pegfilgrastim approximately 10 times the recommended human dose (based on body surface area). In pregnant rabbits, increased embryo lethality and spontaneous abortions occurred at 4 times the maximum recommended human dose simultaneously with signs of maternal toxicity (see Data).

The estimated background risk of major birth defects and miscarriage for the indicated population is unknown. All pregnancies have a background risk of birth defect, loss, or other adverse outcomes. In the U.S. general population, the estimated background risks of major birth defects and miscarriage in clinically recognized pregnancies is 2-4% and 15-20%, respectively.

Data

Animal Data

Pregnant rabbits were dosed with pegfilgrastim subcutaneously every other day during the period of organogenesis. At cumulative doses ranging from the approximate human dose to approximately 4 times the recommended human dose (based on body surface area), the treated rabbits exhibited decreased maternal food consumption, maternal weight loss, as well as reduced fetal body weights and delayed ossification of the fetal skull; however, no structural anomalies were observed in the offspring from either study. Increased incidences of post-implantation losses and spontaneous abortions (more than half the pregnancies) were observed at cumulative doses approximately 4 times the recommended human dose, which were not seen when pregnant rabbits were exposed to the recommended human dose.

Three studies were conducted in pregnant rats dosed with pegfilgrastim at cumulative doses up to approximately 10 times the recommended human dose at the following stages of gestation: during the period of organogenesis, from mating through the first half of pregnancy, and from the first trimester through delivery and lactation. No evidence of fetal loss or structural malformations was observed in any study. Cumulative doses equivalent to approximately 3 and 10 times the recommended human dose resulted in transient evidence of wavy ribs in fetuses of treated mothers (detected at the end of gestation but no longer present in pups evaluated at the end of lactation).

8.2 Lactation

Risk Summary

There are no data on the presence of pegfilgrastim products in human milk, the effects on the breastfed child, or the effects on milk production. Other filgrastim products are secreted poorly into breast milk, and filgrastim products are not absorbed orally by neonates. The developmental and health benefits of breastfeeding should be considered along with the mother’s clinical need for UDENYCA and any potential adverse effects on the breastfed child from UDENYCA or from the underlying maternal condition.

8.4 Pediatric Use

The safety and effectiveness of UDENYCA have been established in pediatric patients. No overall differences in safety were identified between adult and pediatric patients based on postmarketing surveillance and review of the scientific literature.

Use of UDENYCA in pediatric patients for chemotherapy-induced neutropenia is based on UDENYCA's approval as a biosimilar to pegfilgrastim and evidence from adequate and well controlled studies of pegfilgrastim in adults with additional pharmacokinetic and safety data of pegfilgrastim in pediatric patients with sarcoma [see Clinical Pharmacology (12.3) and Clinical Studies (14.1)].

The use of UDENYCA to increase survival in pediatric patients acutely exposed to myelosuppressive doses of radiation is based on UDENYCA's approval as a biosimilar to pegfilgrastim and evidence from efficacy studies of pegfilgrastim conducted in animals and clinical data supporting the use of pegfilgrastim in patients with cancer receiving myelosuppressive chemotherapy. Efficacy studies of pegfilgrastim products could not be conducted in humans with acute radiation syndrome for ethical and feasibility reasons. Results from population modeling and simulation indicate that two doses of pegfilgrastim (Table 1), administered one week apart provide pediatric patients with exposures comparable to that in adults receiving two 6 mg doses one week apart [see Dosage and Administration (2.3), Clinical Pharmacology (12.3) and Clinical Studies (14.2)].

8.5 Geriatric Use

Of the 932 patients with cancer who received pegfilgrastim in clinical studies, 139 (15%) were age 65 and over, and 18 (2%) were age 75 and over. No overall differences in safety or effectiveness were observed between patients age 65 and older and younger patients.

10 OVERDOSAGE

Overdosage of pegfilgrastim products may result in leukocytosis and bone pain. Events of edema, dyspnea, and pleural effusion have been reported in a single patient who administered pegfilgrastim on 8 consecutive days in error. In the event of overdose, the patient should be monitored for adverse reactions [see Adverse Reactions (6)].

11 DESCRIPTION

Pegfilgrastim-cbqv is a covalent conjugate of recombinant methionyl human G-CSF and monomethoxypolyethylene glycol. Recombinant methionyl human G-CSF is a water-soluble, 175 amino acid protein with a molecular weight of approximately 19 kilodaltons (kDa). Recombinant methionyl human G-CSF is obtained from the bacterial fermentation of a strain of E coli transformed with a genetically engineered plasmid containing the human G-CSF gene. During the pegfilgrastim-cbqv manufacturing process, fermentation is carried out in nutrient medium containing the antibiotic kanamycin. However, kanamycin is cleared in the manufacturing process and is not detectable in the final product. To produce pegfilgrastim-cbqv, a 20 kDa monomethoxypolyethylene glycol molecule is covalently bound to the N-terminal methionyl residue of recombinant methionyl human G-CSF. The average molecular weight of pegfilgrastim-cbqv is approximately 39 kDa.

UDENYCA (pegfilgrastim-cbqv) injection is provided in three presentations:

- UDENYCA for manual subcutaneous injection is supplied in 0.6 mL prefilled syringes. The prefilled syringe does not bear graduation marks and is designed to deliver the entire contents of the syringe (6 mg/0.6 mL).
- UDENYCA for subcutaneous injection is supplied in a 0.6 mL prefilled single-dose autoinjector. The prefilled autoinjector delivers the entire contents (6 mg in 0.6mL) in a single injection and is not adjustable.
- On-body injector (OBI) for UDENYCA is supplied with a prefilled syringe containing 0.67 mL of UDENYCA in solution that delivers 0.6 mL of UDENYCA in solution when used with the OBI for UDENYCA. The syringe does not bear graduation marks and is only to be used with the OBI for UDENYCA.

The delivered 0.6 mL dose from either the prefilled syringe for manual subcutaneous injection, the prefilled autoinjector or the OBI for UDENYCA contains 6 mg pegfilgrastim-cbqv (based on protein weight) in a sterile, clear, colorless, preservative-free solution (pH 4.0) containing acetate (0.35 mg), polysorbate 20 (0.02 mg), sodium (0.02 mg), and sorbitol (30 mg) in Water for Injection, USP.

12 CLINICAL PHARMACOLOGY

12.1 Mechanism of Action

Pegfilgrastim products are colony-stimulating factors that act on hematopoietic cells by binding to specific cell surface receptors, thereby stimulating proliferation, differentiation, commitment, and end cell functional activation.

12.2 Pharmacodynamics

Animal data and clinical data in humans suggest a correlation between pegfilgrastim products exposure and the duration of severe neutropenia as a predictor of efficacy. Selection of the dosing regimen of UDENYCA is based on reducing the duration of severe neutropenia.

12.3 Pharmacokinetics

The pharmacokinetics of pegfilgrastim were studied in 379 patients with cancer. The pharmacokinetics of pegfilgrastim were nonlinear, and clearance decreased with increases in dose. Neutrophil receptor binding is an important component of the clearance of pegfilgrastim, and serum clearance is directly related to the number of neutrophils. In addition to numbers of neutrophils, body weight appeared to be a factor. Patients with higher body weights experienced higher systemic exposure to pegfilgrastim after receiving a dose normalized for body weight. A large variability in the pharmacokinetics of pegfilgrastim was observed. The half-life of pegfilgrastim ranged from 15 to 80 hours after subcutaneous injection. In healthy volunteers, the pharmacokinetics of pegfilgrastim were comparable when delivered subcutaneously via a manual prefilled syringe versus via the on-body-injector (OBI) for UDENYCA.

Specific Populations

No gender-related differences were observed in the pharmacokinetics of pegfilgrastim, and no differences were observed in the pharmacokinetics of geriatric patients (≥ 65 years of age) compared with younger patients (< 65 years of age) [see Use in Specific Populations (8.5)].

Renal Impairment

In a study of 30 subjects with varying degrees of renal dysfunction, including end stage renal disease, renal dysfunction had no effect on the pharmacokinetics of pegfilgrastim.

Pediatric Patients with Cancer Receiving Myelosuppressive Chemotherapy

The pharmacokinetics and safety of pegfilgrastim were studied in 37 pediatric patients with sarcoma in Study 4 [see Clinical Studies 14.1]. The mean (± standard deviation [SD]) systemic exposure (AUC0-inf) of pegfilgrastim after subcutaneous administration at 100 mcg/kg was 47.9 (± 22.5) mcg·hr/mL in the youngest age group (0 to 5 years, n = 11), 22.0 (± 13.1) mcg·hr/mL in the 6 to 11 years age group (n = 10), and 29.3 (± 23.2) mcg·hr/mL in the 12 to 21 years age group (n = 13). The terminal elimination half-lives of the corresponding age groups were 30.1 (± 38.2) hours, 20.2 (± 11.3) hours, and 21.2 (± 16.0) hours, respectively.

Patients Acutely Exposed to Myelosuppressive Doses of Radiation

The pharmacokinetics of pegfilgrastim is not available in patients acutely exposed to myelosuppressive doses of radiation. Based on limited pharmacokinetic data in irradiated non-human primates, the area under the concentration-time curve (AUC), reflecting the exposure to pegfilgrastim in non-human primates following a 300 mcg/kg dose of pegfilgrastim, appears to be greater than in humans receiving a 6 mg dose. Results from population modeling and simulation indicate that two 6 mg doses of pegfilgrastim administered one week apart in adults result in clinically relevant effects on duration of grade 3 and 4 neutropenia. In addition, weight-based dosing in pediatric patients weighing less than 45 kg [see Dosage and Administration, Section 2.3, Table 1] provides exposures comparable to those in adults receiving two 6 mg doses one week apart.

13 NONCLINICAL TOXICOLOGY

13.1 Carcinogenesis, Mutagenesis, Impairment of Fertility

No carcinogenicity or mutagenesis studies have been performed with pegfilgrastim products.

Pegfilgrastim did not affect reproductive performance or fertility in male or female rats at cumulative weekly doses approximately 6 to 9 times higher than the recommended human dose (based on body surface area).

14 CLINICAL STUDIES

14.1 Patients with Cancer Receiving Myelosuppressive Chemotherapy

Pegfilgrastim was evaluated in three randomized, double-blind, controlled studies. Studies 1 and 2 were active- controlled studies that employed doxorubicin 60 mg/m^2 and docetaxel 75 mg/m^2 administered every 21 days for up to 4 cycles for the treatment of metastatic breast cancer. Study 1 investigated the utility of a fixed dose of pegfilgrastim. Study 2 employed a weight-adjusted dose. In the absence of growth factor support, similar chemotherapy regimens have been reported to result in a 100% incidence of severe neutropenia (ANC < 0.5 x 10^9/L) with a mean duration of 5 to 7 days and a 30% to 40% incidence of febrile neutropenia. Based on the correlation between the duration of severe neutropenia and the incidence of febrile neutropenia found in studies with filgrastim, duration of severe neutropenia was chosen as the primary endpoint in both studies, and the efficacy of pegfilgrastim was demonstrated by establishing comparability to filgrastim-treated patients in the mean days of severe neutropenia.

In Study 1, 157 patients were randomized to receive a single subcutaneous injection of pegfilgrastim (6 mg) on day 2 of each chemotherapy cycle or daily subcutaneous filgrastim (5 mcg/kg/day) beginning on day 2 of each chemotherapy cycle. In Study 2, 310 patients were randomized to receive a single subcutaneous injection of pegfilgrastim (100 mcg/kg) on day 2 or daily subcutaneous filgrastim (5 mcg/kg/day) beginning on day 2 of each chemotherapy cycle.

Both studies met the major efficacy outcome measure of demonstrating that the mean days of severe neutropenia of pegfilgrastim-treated patients did not exceed that of filgrastim-treated patients by more than 1 day in cycle 1 of chemotherapy. The mean days of cycle 1 severe neutropenia in Study 1 were 1.8 days in the pegfilgrastim arm compared to 1.6 days in the filgrastim arm [difference in means 0.2 (95% CI -0.2, 0.6)] and in Study 2 were 1.7 days in the pegfilgrastim arm compared to 1.6 days in the filgrastim arm [difference in means 0.1 (95% CI -0.2, 0.4)].

A secondary endpoint in both studies was days of severe neutropenia in cycles 2 through 4 with results similar to those for cycle 1.

Study 3 was a randomized, double-blind, placebo-controlled study that employed docetaxel 100 mg/m^2 administered every 21 days for up to 4 cycles for the treatment of metastatic or non-metastatic breast cancer. In this study, 928 patients were randomized to receive a single subcutaneous injection of pegfilgrastim (6 mg) or placebo on day 2 of each chemotherapy cycle. Study 3 met the major trial outcome measure of demonstrating that the incidence of febrile neutropenia (defined as temperature ≥ 38.2°C and ANC ≤ 0.5 x109/L) was lower for pegfilgrastim-treated patients as compared to placebo-treated patients (1% versus 17%, respectively, p < 0.001). The incidence of hospitalizations (1% versus 14%) and IV anti-infective use (2% versus 10%) for the treatment of febrile neutropenia was also lower in the pegfilgrastim-treated patients compared to the placebo-treated patients.

Study 4 was a multicenter, randomized, open-label study to evaluate the efficacy, safety, and pharmacokinetics [see Clinical Pharmacology (12.3)] of pegfilgrastim in pediatric and young adult patients with sarcoma. Patients with sarcoma receiving chemotherapy age 0 to 21 years were eligible. Patients were randomized to receive subcutaneous pegfilgrastim as a single dose of 100 mcg/kg (n= 37) or subcutaneous filgrastim at a dose 5 mcg/kg/day (n=6) following myelosuppressive chemotherapy. Recovery of neutrophil counts was similar in the pegfilgrastim and filgrastim groups. The most common adverse reaction reported was bone pain.

14.2 Patients with Hematopoietic Subsyndrome of Acute Radiation Syndrome

Efficacy studies of pegfilgrastim products could not be conducted in humans with acute radiation syndrome for ethical and feasibility reasons. Approval of this indication was based on efficacy studies conducted in animals and data supporting pegfilgrastim's effect on severe neutropenia in patients with cancer receiving myelosuppressive chemotherapy [see Dosage and Administration (2.1)].

The recommended dose of UDENYCA is two doses, 6 mg each, administered one week apart for humans exposed to myelosuppressive doses of radiation. For pediatric patients weighing less than 45 kg, dosing of UDENYCA is weight based and is provided in Table 1 [see Dosage and Administration (2.3)]. This dosing regimen is based on population modeling and simulation analyses. The exposure associated with this dosing regimen is expected to provide sufficient pharmacodynamic activity to treat humans exposed to myelosuppressive doses of radiation [see Clinical Pharmacology (12.3)]. The safety of pegfilgrastim at a dose of 6 mg has been assessed on the basis of clinical experience in patients with cancer receiving myelosuppressive chemotherapy.

The efficacy of pegfilgrastim for the acute radiation syndrome setting was studied in a randomized, placebo- controlled non-human primate model of radiation injury. Rhesus macaques were randomized to either a control (n = 23) or treated (n = 23) cohort. On study day 0, animals (n = 6 to 8 per irradiation day) were exposed to total body irradiation (TBI) of 7.50 ± 0.15 Gy delivered at 0.8 ± 0.03 Gy/min, representing a dose that would be lethal in 50% of animals by 60 days of follow-up (LD50/60). Animals were administered subcutaneous injections of a blinded treatment (control article [5% dextrose in water] or pegfilgrastim [300-319 mcg/kg/day]) on study day 1 and on study day 8. The primary endpoint was survival. Animals received medical management consisting of intravenous fluids, antibiotics, blood transfusions, and other support as required.

Pegfilgrastim significantly (at 0.0014 level of significance) increased 60-day survival in irradiated non-human primates: 91% survival (21/23) in the pegfilgrastim group compared to 48% survival (11/23) in the control group.

16 HOW SUPPLIED/STORAGE AND HANDLING

UDENYCA single-dose prefilled syringe for manual use

UDENYCA (pegfilgrastim-cbqv) injection is a clear, colorless, preservative-free solution supplied in a prefilled single-dose syringe containing 6 mg pegfilgrastim-cbqv, supplied with a 29-gauge, 1⁄2-inch needle with an UltraSafe Passive™ Needle Guard.

The needle cap of the prefilled syringe is not made with natural rubber latex.

UDENYCA is provided in a dispensing pack containing one sterile 6 mg/0.6 mL prefilled syringe (NDC 70114-101-01).

UDENYCA prefilled syringe does not bear graduation marks and is intended only to deliver the entire contents of the syringe (6 mg/0.6 mL) for direct administration. Use of the prefilled syringe is not recommended for direct administration for pediatric patients weighing less than 45 kg who require doses that are less than the full contents of the syringe.

Store refrigerated between 2° to 8°C (36° to 46°F) in the carton to protect from light. Do not shake. Discard UDENYCA stored at room temperature for more than 48 hours. Avoid freezing; if frozen, thaw in the refrigerator before administration. Discard UDENYCA if frozen more than once.

UDENYCA single-dose prefilled autoinjector

UDENYCA (pegfilgrastim-cbqv) injection is a clear, colorless, preservative-free solution supplied in a prefilled single-dose autoinjector containing 6 mg pegfilgrastim-cbqv.

The needle cap of the prefilled autoinjector is not made with natural rubber latex.

UDENYCA is provided in a dispensing pack containing one 6 mg/0.6 mL prefilled autoinjector (NDC 70114-120-01).

The UDENYCA prefilled autoinjector is not suitable for use in pediatric patients weighing less than 45 kg. The UDENYCA prefilled autoinjector delivers the entire contents (6 mg in 0.6 mL) in a single injection and is not adjustable.

Store refrigerated between 2° to 8°C (36° to 46°F) in the carton to protect from light. Do not shake. Discard UDENYCA stored at room temperature for more than 48 hours. Avoid freezing; if frozen, thaw in the refrigerator before administration. Discard UDENYCA if frozen more than once.

UDENYCA ONBODY

UDENYCA ONBODY is provided in a carton containing one sterile prefilled syringe and one sterile on-body injector (OBI) for UDENYCA (NDC 70114-130-01).

The UDENYCA injection single-dose prefilled syringe contains 0.67 mL of a clear, colorless solution that delivers 6 mg/0.6 mL of pegfilgrastim-cbqv when used with the OBI for UDENYCA. The prefilled syringe is supplied with a 29-gauge, 1/2-inch needle. The syringe does not bear graduation marks and is only to be used with the OBI for UDENYCA.

The needle cap of the prefilled syringe is not made with natural rubber latex.

Store UDENYCA ONBODY in the refrigerator at 2°C to 8°C (36°F to 46°F) until 30 minutes prior to use. Because the OBI for UDENYCA is at room temperature during the period of use, UDENYCA ONBODY should not be held at room temperature longer than 12 hours prior to use. Discard UDENYCA ONBODY if stored at room temperature for more than 12 hours.

Do not use the OBI for UDENYCA if its packaging has been previously opened.

17 PATIENT COUNSELING INFORMATION

Advise the patient to read the FDA-approved patient labeling (Patient Information and Instructions for Use)

Advise patients of the following risks and potential risks with UDENYCA:

- Splenic rupture and splenomegaly
- Acute Respiratory Distress Syndrome
- Serious allergic reactions
- Sickle cell crisis
- Glomerulonephritis
- Increased risk of Myelodysplastic Syndrome and/or Acute Myeloid Leukemia in patients with breast and lung cancer who receive UDENYCA in conjunction with chemotherapy and/or radiation therapy
- Capillary Leak Syndrome
- Aortitis

Advise patients acutely exposed to myelosuppressive doses of radiation (Hematopoietic Subsyndrome of Acute Radiation Syndrome) that efficacy studies of pegfilgrastim products for this indication could not be conducted in humans for ethical and feasibility reasons and that, therefore, approval of this use was based on efficacy studies conducted in animals [see Clinical Studies (14.2)].

Instruct patients who self-administer UDENYCA using the single-dose prefilled syringe of the:

- Importance of following the Instructions for Use (see Instructions for Use).
- Dangers of reusing syringes.
- Importance of following local requirements for proper disposal of used syringes.

For patients who will use the UDENYCA prefilled autoinjector, tell them that they:

- Will hear two "clicks" during the UDENYCA injection. The first 'click' means the start of injection and second 'click' means the end of injection.
- To start injection, push the prefilled autoinjector body down. Continue holding down after hearing the first 'click'.
- In the viewing window, the orange indicator will advance to show the progress of the injection.

When injection has finished, there will be a second 'click' and the 'Orange Indicator' will completely block the viewing window.

Advise patients on the use of the on-body injector (OBI) for UDENYCA:

- Review the Patient Information and Patient Instructions for Use with the patient and provide the instructions to the patient.
- Refer the patient to the dose delivery information written on the Patient Instructions for Use.
- Tell the patient when their dose delivery of UDENYCA will begin and when their dose delivery should be completed.
- Advise the patient that serious allergic reactions can happen with UDENYCA. Patients should have a caregiver nearby for the first use. Patients should plan to be in a place where they can appropriately monitor the OBI for UDENYCA during the approximately 5 minutes UDENYCA delivery and for an hour after the delivery. Advise the patient to avoid traveling, driving, or operating heavy machinery during hours 26-29 following application of the OBI for UDENYCA.
- If the OBI for UDENYCA is placed on the back of the arm, remind the patient that a caregiver must be available to monitor the OBI for UDENYCA.
- If a patient calls the healthcare provider regarding any OBI for UDENYCA problems, the healthcare provider is advised to call Coherus at 1-800-483-3692.
- Advise the patient:
  - to call their healthcare provider immediately if the status light on the OBI for UDENYCA is flashing red (see the Patient Instructions for Use).
  - to inform their healthcare provider if the adhesive on the OBI for UDENYCA becomes saturated with fluid, or there is dripping, as this may be evidence of significant product leakage, resulting in inadequate or missed dose (see the Patient Instructions for Use).
  - to keep the OBI for UDENYCA dry for approximately the last 3 hours prior to the dose delivery start to better enable potential leak detection.
  - that the OBI for UDENYCA should only be exposed to temperatures between 41°F and 104°F (5°C to 40°C).
  - to keep the OBI for UDENYCA at least 4 inches away from electrical equipment such as cell phones, cordless telephones, microwaves, and other common appliances. Failure to keep the OBI for UDENYCA at least this recommended distance may interfere with operation and can lead to a missed or incomplete dose of UDENYCA.
  - that if the needle is exposed after OBI for UDENYCA removal, place the used OBI for UDENYCA in a sharps disposal container to avoid accidental needle stick and call their healthcare provider immediately.
  - to remove the OBI for UDENYCA after the green light shines continuously and to place the used OBI for UDENYCA in a sharps disposal container (see the Patient Instructions for Use).
- Advise the patient:
  - do not reapply the OBI for UDENYCA if the OBI for UDENYCA comes off before full dose is delivered and instead call their healthcare provider immediately, as they may need a replacement dose.
  - avoid bumping the OBI for UDENYCA or knocking the OBI for UDENYCA off the body.
  - do not use other materials to hold the on-body injector in place that could cover audio/visual indicators or compress the on-body injector against the patient’s skin, as this could dislodge the cannula and lead to a missed dose or incomplete dose of UDENYCA.
  - do not expose the OBI for UDENYCA to medical imaging studies (e.g., X-ray scan, MRI, CT scan and ultrasound), radiation treatment, and oxygen rich environments such as hyperbaric chambers to avoid OBI for UDENYCA damage and patient injury.
- Advise the patient to avoid:
  - airport X-ray scans and request a manual pat down instead; remind patients who elect to request a manual pat down to exercise care to avoid having the OBI for UDENYCA dislodged during the pat down process.
  - sleeping on the OBI for UDENYCA or applying pressure on the OBI for UDENYCA as this may affect OBI for UDENYCA performance.
  - getting body lotions, creams, oils, and cleaning agents near the OBI for UDENYCA as these products may loosen the adhesive.
  - use of lotions, creams, or oils on their arms and abdomen prior to their next scheduled OBI for UDENYCA dose (to help with device adherence to the skin).
  - using bath tubs, hot tubs, whirlpools, or saunas and avoid exposing the OBI for UDENYCA to direct sunlight as these may affect the drug.
  - peeling off or disturbing the OBI for UDENYCA adhesive before delivery of full dose is complete.

Coherus
BioSciences

UDENYCA® (pegfilgrastim-cbqv)

Manufactured by: Coherus BioSciences, Inc., Redwood City, California 94065-1442
U.S. License No. 2023

© 2021 Coherus BioSciences Inc. All rights reserved.

For more information, go to www.UDENYCA.com or call 1-800-4UDENYCA (1-800-483-3692)

PMD-0212, Rev. 00

Patient Information
UDENYCA® (yoo-den-i-kah)
(pegfilgrastim-cbqv)
Injection

What is UDENYCA?
UDENYCA is a man-made form of granulocyte colony-stimulating factor (G-CSF). G-CSF is a substance produced by the body. It stimulates the growth of neutrophils, a type of white blood cell important in the body’s fight against infection.
Acute Radiation Syndrome: The effectiveness of pegfilgrastim for this use was only studied in animals, because it could not be studied in people.

Do not take UDENYCAif you have had a serious allergic reaction to pegfilgrastim products or filgrastim products.

Before you receive UDENYCA, tell your healthcare provider about all of your medical conditions, including if you:

- have a sickle cell disorder.
- have kidney problems.
- are pregnant or plan to become pregnant. It is not known if UDENYCA will harm your unborn baby.
- are breastfeeding or plan to breastfeed. It is not known if UDENYCA passes into your breast milk.

Tell your healthcare provider about all of the medicines you take, including prescription and over-the-counter medicines, vitamins, and herbal supplements.

How will I receive UDENYCA?

- UDENYCA is given as an injection under your skin (subcutaneous injection) by a healthcare provider. If your healthcare provider decides that the subcutaneous injections can be given at home by you or your caregiver, follow the detailed "Instructions for Use" that comes with your UDENYCA for information on how to prepare and inject a dose of UDENYCA.
- You and your caregiver will be shown how to prepare and inject UDENYCA before you use it.
- UDENYCA comes in a prefilled syringe or a prefilled autoinjector. Your healthcare provider will prescribe the type of UDENYCA that is right for you.
- Only adults can self-inject UDENYCA with the prefilled autoinjector.
- You should not inject a dose of UDENYCA to children weighing less than 45 kg from a UDENYCA prefilled syringe. or prefilled autoinjector. A dose less than 0.6 mL (6 mg) cannot be accurately measured using the UDENYCA prefilled syringe or prefilled autoinjector.
- If you are receiving UDENYCA because you are also receiving chemotherapy, the last dose of UDENYCA should be injected at least 14 days before and 24 hours after your dose of chemotherapy.
- If you miss a dose of UDENYCA, talk to your healthcare provider about when you should give your next dose.
- When using the UDENYCA prefilled autoinjector:
  - You may miss your dose or may not receive your full dose if you lift the prefilled autoinjector before you hear the second "click" or if the orange indicator does not completely fill the viewing window.
  - Call your healthcare provider right away if this happens, as you may need a replacement dose of UDENYCA.

What are possible side effects of UDENYCA?
UDENYCA may cause serious side effects, including:

- Spleen rupture. Your spleen may become enlarged and can rupture. A ruptured spleen can cause death. Call your healthcare provider right away if you have pain in the left upper stomach area or your left shoulder.
- A serious lung problem called Acute Respiratory Distress Syndrome (ARDS). Call your healthcare provider or get emergency help right away if you have shortness of breath with or without a fever, trouble breathing, or a fast rate of breathing.
- Serious allergic reactions. UDENYCA can cause serious allergic reactions. These reactions can cause a rash over your whole body, shortness of breath, wheezing, dizziness, swelling around your mouth or eyes, fast heart rate, and sweating. If you have any of these symptoms, stop using UDENYCA and call your healthcare provider or get emergency medical help right away.
- Sickle cell crises. You may have a serious sickle cell crisis, which could lead to death, if you have a sickle cell disorder and receive UDENYCA. Serious sickle cell crises have happened in people with sickle cell disorders receiving pegfilgrastim that has sometimes led to death. Call your healthcare provider right away if you have symptoms of sickle cell crisis such as pain or difficulty breathing.
- Kidney injury (glomerulonephritis). UDENYCA can cause kidney injury. Call your healthcare provider right away if you develop any of the following symptoms:
  - swelling of your face or ankles
  - blood in your urine or dark colored urine
  - you urinate less than usual
- Increased white blood cell count (leukocytosis). Your healthcare provider will check your blood during treatment with UDENYCA.
- Decreased platelet count (thrombocytopenia). Your healthcare provider will check your blood during treatment with UDENYCA. Tell your healthcare provider if you have unusual bleeding or bruising during treatment with UDENYCA. This could be a sign of decreased platelet counts, which may reduce the ability of your blood to clot.
- Capillary Leak Syndrome. UDENYCA can cause fluid to leak from blood vessels into your body’s tissues. This condition is called "Capillary Leak Syndrome" (CLS). CLS can quickly cause you to have symptoms that may become life-threatening. Get emergency medical help right away if you develop any of the following symptoms:
  - swelling or puffiness and are urinating less than usual
  - trouble breathing
  - swelling of your stomach-area (abdomen) and feeling of fullness
  - dizziness or feeling faint
  - a general feeling of tiredness
- Myelodysplastic syndrome and acute myeloid leukemia. If you have breast cancer or lung cancer, when UDENYCA is used with chemotherapy and radiation therapy, or with radiation therapy alone, you may have an increased risk of developing a precancerous blood condition called myelodysplastic syndrome (MDS) or a blood cancer called acute myeloid leukemia (AML).Symptoms of MDS and AML may include tiredness, fever, and easy bruising or bleeding. Call your healthcare provider if you develop these symptoms during treatment with UDENYCA.
- Inflammation of the aorta (aortitis). Inflammation of the aorta (the large blood vessel that transports blood from the heart to the body) has been reported in patients who received pegfilgrastim. Symptoms may include fever, abdominal pain, feeling tired, and back pain. Call your healthcare provider if you experience these symptoms.

The most common side effects of UDENYCA are pain in the bones, arms, and legs.
These are not all the possible side effects of UDENYCA.
Call your doctor for medical advice about side effects. You may report side effects to FDA at 1-800-FDA-1088.

How should I store UDENYCA?

- Store UDENYCA in the refrigerator between 36°F to 46°F (2°C to 8°C).
- Do not freeze. If UDENYCA is accidentally frozen, allow it to thaw in the refrigerator before injecting.
- Do not use UDENYCA that has been frozen more than 1 time. Use a new UDENYCA prefilled syringe or prefilled autoinjector.
- Throw away (dispose of) any UDENYCA that has been left at room temperature, 68ºF to 77ºF (20ºC to 25ºC), for more than 48 hours or frozen more than 1 time.
- Keep UDENYCA in the original carton to protect from light.
- Do not shake UDENYCA.
- Take UDENYCA out of the refrigerator 30 minutes before use and allow it to reach room temperature before preparing an injection.

Keep UDENYCA out of the reach of children.

General information about the safe and effective use of UDENYCA.
Medicines are sometimes prescribed for purposes other than those listed in a Patient Information leaflet. Do not use UDENYCA for a condition for which it was not prescribed. Do not give UDENYCA to other people, even if they have the same symptoms that you have. It may harm them. You can ask your pharmacist or healthcare provider for information about UDENYCA that is written for health professionals.

What are the ingredients in UDENYCA?
Active ingredient: pegfilgrastim-cbqv
Inactive ingredients: acetate, polysorbate 20, sodium, and sorbitol in Water for Injection.

Manufactured by: Coherus BioSciences, Inc., Redwood City, California 94065-1442
U.S. License No. 2023
© 2023 Coherus BioSciences Inc. All rights reserved.
For more Information go to www.UDENYCA.com or call 1-800-4UDENYCA (1-800-483-3692)
PMD-0006 Rev. 06

Coherus
BioSciences

This Patient Information has been approved by the U.S. Food and Drug Administration

Revised: 03/2023

Instructions for Use
UDENYCA® (yoo-den-i-kah)
(pegfilgrastim-cbqv)
Injection
Single-Dose Prefilled Syringe

Guide to Parts

Before Use

Important: The needle is covered by a needle cap before use

After Use

Important
Read the Patient Information for important information you need to know about
UDENYCA before using these Instructions for Use.

Storing the UDENYCA prefilled syringe

- Store UDENYCA prefilled syringes in the refrigerator between 36°F to 46° F (2°C to 8°C).
- Keep the UDENYCA prefilled syringe in the original carton to protect from light.
- Do not freeze UDENYCA.
  - If UDENYCA is accidentally frozen, allow the prefilled syringe to thaw in the refrigerator before injecting.
  - Throw away (dispose of) any UDENYCA prefilled syringes that have been frozen more than 1 time.
- Throw away (dispose of) any UDENYCA prefilled syringes that have been left out at room temperature for more than 48 hours.
- Keep the UDENYCA prefilled syringe out of the reach of children.

Using the prefilled syringe

- It is important that you do not try to give the injection unless you or your caregiver has received training from your healthcare provider.
- Make sure that the name UDENYCA appears on the carton and prefilled syringe label.
- Check the carton and prefilled syringe label to make sure the dose strength is 6 mg/0.6 mL.
- You should not inject a dose of UDENYCA to children weighing less than 45 kg from a UDENYCA prefilled syringe. A dose less than 0.6 mL (6 mg) cannot be accurately measured using the UDENYCA prefilled syringe.
- Do not use a prefilled syringe after the expiration date on the label.
- Do not shake the prefilled syringe
- Do not remove the needle cap from the prefilled syringe until you are ready to inject.
- Do not use the prefilled syringe if the carton is open or damaged.
- Do not use a prefilled syringe if it has been dropped on a hard surface. The prefilled syringe may be broken even if you cannot see the break. Use a new prefilled syringe.
- Do not attempt to activate the needle safety guard prior to injection

Call your healthcare provider if you have any questions.

Prepare the injection

1 - Remove carton from refrigerator and check expiration date

1A: Remove the carton from the refrigerator and check the expiration date printed on the carton. (See Figure 3)
Do not use if the expiration date has passed.

1B: Open the carton and remove the sealed syringe tray. (See Figure 4)

2 - Allow UDENYCA to reach room temperature and gather supplies

2A: Place the sealed syringe tray on a flat, clean work surface and allow it to sit at room temperature for at least 30 minutes. (See Figure 5)
Do not attempt to warm up the syringe in any other way, such as a microwave, hot water, or direct sunlight.

2B: Gather the following supplies: (See Figure 6)

- Alcohol wipe
- Cotton ball or gauze
- 1 adhesive bandage
- Sharps disposal container

3 - Wash your hands and remove syringe from tray

3A: Wash your hands well with soap and warm water. (See Figure 7)

3B: Open the tray by peeling away the cover. Remove the prefilled syringe from the tray by grasping the middle of the syringe body and carefully pulling it out of the tray. (See Figure 8)
For Safety reasons:

- Do not grab the plunger or the plunger head.
- Do not grab the needle cap.

4 - Inspect the syringe and medicine

Check the medicine through the Inspection Window. The medicine should be clear and colorless. It is normal to see 1 or more air bubbles in the syringe. Removal of the air is not needed. (See Figure 9)
Do not use the prefilled syringe if:

- the medicine appears discolored or cloudy.
- the medicine contains lumps, flakes, or particles.
- it appears used or damaged.
- the needle cap is missing or not securely attached.
- the expiration date printed on the label has passed.

In all cases, use a new prefilled syringe and call your healthcare provider.

Select and clean injection site

5 - Select and clean the injection site

5A: Select the injection site. The recommended injection sites for a subcutaneous injection are the: (See Figure 10)

- Abdomen (except for a two-inch area surrounding the navel)
- Thighs
- Back of upper arms (only if someone else is giving you the injection)
- Upper outer area of the buttocks (only if someone else is giving you the injection)

Do not inject into moles, scars, birthmarks, or areas where the skin is tender, bruised, red, or hard.
If you want to use the same injection site, make sure it is not the same spot on the injection site you used for a previous injection.

5B: Clean the injection site with an alcohol wipe. (See Figure 11)
Do not touch this area again before injection.

Inject the dose

6 - Remove needle cap

Remove the needle cap by pulling it straight off. (See Figure 12)

- Do not remove the needle cap from the prefilled syringe until you are ready to inject.
- Do not twist or bend the needle cap.
- Do not hold the prefilled syringe by the plunger rod
- Do not put the needle cap back onto the syringe. Dispose of (throw away) the needle cap in your household trash
- Do not use the prefilled syringe if it has been dropped with the needle cap removed.

7 – Position fingers

Grasp the body of the syringe like a dart (just under the finger grips) with your thumb and index fingers. (See Figure 13)

- Do not touch the plunger or grasp the syringe above the finger grips.

8 – Pinch the skin and insert the needle

8A: Use your free hand to gently pinch the cleaned injection site to create a firm surface. (See Figure 14)

8B: Hold the pinch. Insert the needle into the skin at a 45 to 90-degree angle. (See Figure 15)

- Do not touch the plunger head while inserting the needle into the skin.
- Do not touch the cleaned area of the skin

8C: After fully inserting the needle, release the pinched skin and use your free hand to stabilize the bottom of the syringe.
Then move your other hand into injection position with your thumb on the plunger head. (See Figure 16)

9 – Push plunger head down to deliver dose

9A: Using slow and constant pressure, push the plunger head down until it reaches the bottom. This will help to ensure that you receive the full dose. (See Figure 17)

9B: While the needle is still inserted, slowly move your thumb back, allowing the plunger to rise. This will release the needle safety guard to safely cover the needle. Then remove the syringe from the injection site. (See Figure 18)
Important: When you remove the syringe, if it looks like the medicine is still in the syringe, this means you have not received a full dose. Call your healthcare provider right away.

- If you see drops of blood at the injection site, treat by pressing a cotton ball or gauze to the site as needed.

Dispose

10 – Dispose of used prefilled syringes

Put the used prefilled syringe into an FDA-cleared sharps disposal container right away after use. Do not throw away the syringe in the household trash. (See Figure 19)

- If you do not have a FDA-cleared sharps disposal container, you may use a household container that is:
  - made of a heavy-duty plastic
  - can be closed with a tight-fitting, puncture-resistant lid, without sharps being able to come out
  - upright and stable during use
  - leak-resistant
  - properly labeled to warn of hazardous waste inside the container
- When your sharps disposal container is almost full, you will need to follow your community guidelines for the right way to dispose of your sharps disposal container. There may be state or local laws about how you should throw away used needles and syringes. For more information about safe sharps disposal, and for specific information about sharps disposal in the state that you live in, go to the FDA's website at: http://www.fda.gov/safesharpsdisposal.
- Do not reuse the prefilled syringe.
- Do not recycle prefilled syringes or sharps disposal container or throw them into household trash.

This Instructions for Use has been approved by the U.S. Food and Drug Administration.

Issued: 09/2019

Coherus
BioSciences

UDENYCA® (pegfilgrastim-cbqv)
Manufactured by: Coherus BioSciences, Inc., Redwood City, California 94065-1442
U.S. License No. 2023
© 2019 Coherus BioSciences Inc. All rights reserved.

For more Information go to www.UDENYCA.com or call 1-800-4UDENYCA (1-800-483-3692)

PMD-0005, Rev. 02

INSTRUCTIONS FOR USE
UDENYCA™ (yoo-den-i-kah)
(pegfilgrastim-cbqv)
injection, for subcutaneous use
Single-Dose Prefilled Autoinjector

Storing the UDENYCA prefilled autoinjector

- Store UDENYCA prefilled autoinjector in the refrigerator between 36°F to 46°F (2°C to 8°C).
- Keep the UDENYCA prefilled autoinjector in the original carton to protect from light.
- Do not freeze UDENYCA.
  - If UDENYCA is accidentally frozen, allow the prefilled autoinjector to thaw in the refrigerator before injecting.
  - Throw away (dispose of) any UDENYCA prefilled autoinjectors that have been frozen more than 1 time.
- Throw away (dispose of) any UDENYCA prefilled autoinjectors that have been left out at room temperature for more than 48 hours.
- Keep the UDENYCA prefilled autoinjector out of the reach of children.

Using the UDENYCA prefilled autoinjector

- It is important that you do not try to give the injection unless you or your caregiver has received training from your healthcare provider.
- Only adults can self-inject UDENYCA with the prefilled autoinjector.
- Make sure that the name UDENYCA appears on the carton and prefilled autoinjector label.
- Check the carton and prefilled autoinjector label to make sure the dose strength is 6 mg/0.6 mL.
- You should not inject a dose of UDENYCA to children weighing less than 45 kg from an UDENYCA prefilled autoinjector. A dose less than 0.6 mL (6 mg) cannot be accurately measured using the UDENYCA prefilled autoinjector.
- Do not use a prefilled autoinjector after the expiration date on the label.
- Do not shake the prefilled autoinjector.
- Do not remove the clear cap from the prefilled autoinjector until you are ready to inject.
- Do not use the prefilled autoinjector if the carton is open or damaged.
- Do not use a prefilled autoinjector if it has been dropped on a hard surface. The prefilled autoinjector may be broken even if you cannot see the break. Use a new prefilled autoinjector.

Call your healthcare provider if you have any questions.

Take the UDENYCA carton out of the refrigerator.

- Leave the prefilled autoinjector in the carton at room temperature for 30 minutes before injecting.
- Do not remove the clear cap while allowing the prefilled autoinjector to reach room temperature.
- Do not warm the prefilled autoinjector in any other way. For example, do not warm it in a microwave, in hot water, or in direct sunlight.

Check the expiration date on the prefilled autoinjector label. Do not use the prefilled autoinjector if the expiration date has passed. Place the following supplies on a clean, flat surface:

- 1 single-dose UDENYCA prefilled autoinjector
- 1 alcohol wipe (not included)
- 1 cotton ball or gauze pad (not included)
- 1 sharps disposal container (not included). See "How should I throw away (dispose of) the used UDENYCA prefilled autoinjector?" in step 10.

Wash and dry your hands.

Choose an injection site.

- abdomen (except for a two-inch area surrounding the navel)
- thighs

If someone else is giving you the injection, you can also use the:

- back of upper arms
- upper outer area of the buttocks
- Do not inject into moles, scars, birthmarks, or areas where the skin is tender, bruised, red, or hard.
- Change (rotate) your injection site with each injection.
- Do not inject through clothing. Clean the injection site with an alcohol wipe. Let your skin air dry. Do not touch this area again before injection.

Check the viewing window:

- Hold the prefilled autoinjector with the clear cap facing down.
- It is normal to see 1 or more air bubbles in the viewing window.
- Make sure the liquid is clear and colorless.

Do not use the prefilled autoinjector if:

- the medicine appears discolored or cloudy.
- the medicine contains lumps, flakes, or particles.
- if it has been dropped, crushed or damaged in any way.

Hold the prefilled autoinjector with the clear cap facing up and pull the clear cap straight off.

- It is normal to see a few drops of liquid at the end of the needle.
- Throw away the clear cap.
- Do not put the clear cap back on the prefilled autoinjector after it has been removed.
- Do not touch the gray needle guard.

Hold the body of the prefilled autoinjector in one hand so you can see the viewing window.
Place the gray needle guard against your skin at a 90-degree angle.

Press the prefilled autoinjector firmly against the skin and you will hear the first "click".
The orange indicator will start to move along the viewing window.

Keep holding the prefilled autoinjector firmly against the skin until the orange indicator stops moving and you hear the second "click".
After you hear the second "click", continue to hold the prefilled autoinjector in place and count to 5.
When the injection is complete, make sure the orange indicator completely fills the viewing window before slowly lifting the prefilled autoinjector away from the skin.

The gray needle guard will cover the needle tip.
If the viewing window is not completely filled by the orange indicator or if there are more than a few drops of liquid on the injection site, contact your healthcare provider right away. You may not have received your full dose.
After completing the injection, place a cotton ball or gauze pad over the injection site.

- Do not rub the injection site.
- Slight bleeding at the injection site is normal.

How should I throw away (dispose of) the used UDENYCA prefilled autoinjector?

- Put your used prefilled autoinjector in a FDA-cleared sharps disposal container right away after use. Do not throw away (dispose of) prefilled autoinjectors in the household trash.
- If you do not have a FDA-cleared sharps disposal container, you may use a household container that is:
  - made of a heavy-duty plastic,
  - can be closed with a tight-fitting, puncture-resistant lid, without sharps being able to come out,
  - upright and stable during use,
  - leak-resistant, and
  - properly labeled to warn of hazardous waste inside the container.
- When your sharps disposal container is almost full, you will need to follow your community guidelines for the right way to dispose of your sharps disposal container. There may be state or local laws about how you should throw away used prefilled autoinjectors. For more information about safe sharps disposal, and for specific information about sharps disposal in the state that you live in, go to the FDA's website at: http://www.fda.gov/safesharpsdisposal.
- Do not dispose of your used sharps disposal container in your household trash unless your community guidelines permit this. Do not reuse the prefilled autoinjector. Do not recycle your used sharps disposal container.

Important: Always keep the sharps disposal container out of reach of children.

- The clear cap, alcohol swab, cotton ball or gauze pad, and packaging may be placed in your household trash.

This Instructions for Use has been approved by the U.S. Food and Drug Administration.

Issued: 03/2023

Manufactured by: Coherus BioSciences, Inc., Redwood City California 94065-1442
U.S. License No. 2023
©2023 Coherus BioSciences, Inc. All rights reserved.
For more information, go to www.UDENYCA.com, or call 1-800-4UDENYCA (1-800-483-3692)
PMD-0175 Rev. 00

Coherus
BIOSCIENCES

Patient Information
UDENYCA® (yoo-den-i-kah)
(pegfilgrastim-cbqv)
injection
on-body injector for UDENYCA

What is the most important information I need to know about receiving UDENYCA with the on-body injector for UDENYCA?

- See the Instructions for Use for the on-body injector for UDENYCA for detailed information about the on-body injector for UDENYCA and important information about your dose delivery that has been written by your healthcare provider.
  - Know the time that delivery of your dose of UDENYCA is expected to start.
  - Avoid traveling, driving, or operating heavy machinery during hour 26 through hour 29 after the on-body injector for UDENYCA is applied. Avoid activities and places that may interfere with monitoring during the 5-minute period that UDENYCA is expected to be delivered by the on-body injector for UDENYCA, and for 1 hour after delivery.
- A caregiver should be with you the first time that you receive UDENYCA with the on-body injector for UDENYCA.
- Before your next scheduled UDENYCA dose, avoid use of lotions, creams, or oils on your arms and stomach area (abdomen) to help keep the device on your skin.
- If placed on the back of the arm, a caregiver must be available to monitor the status of the on-body injector.
- If you have an allergic reaction during the delivery of UDENYCA, remove the on-body injector for UDENYCA by grabbing the edge of the adhesive pad and peeling off the on-body injector for UDENYCA. Get emergency medical help right away.
- You should only receive a dose of UDENYCA on the day your healthcare provider tells you.
- You should not receive your dose of UDENYCA any sooner than 24 hours after you finish receiving your chemotherapy. The on-body injector for UDENYCA is programmed to deliver your dose about 27 hours after your healthcare provider fills and places the on-body injector for UDENYCA on your skin.
- Do not expose the on-body injector for UDENYCA to the following because the on-body injector for UDENYCA may be damaged, and you could be injured:
  - Diagnostic imaging (e.g., CT scan, MRI, Ultrasound, X-ray)
  - Radiation treatment
  - Oxygen rich environments, such as hyperbaric chambers
- Avoid airport X-ray scans. Request a manual pat down instead. Use care during a manual pat down to help prevent the on-body injector for UDENYCA from being accidentally removed.
- Keep the on-body injector for UDENYCA at least 4 inches away from electrical equipment such as cell phones, cordless telephones, microwaves and other common appliances. If the on-body injector for UDENYCA is too close to electrical equipment, it may not work correctly and can lead to a missed or incomplete dose of UDENYCA.
- The on-body injector is for adult patients only.
- If your on-body injector is not working properly, you may miss your dose or you may not receive your full dose of UDENYCA. If you miss your dose or do not receive your full dose of UDENYCA, you may have an increased risk of developing fever or infection.
- Call your healthcare provider right away, as you may need a replacement dose, if any of the following occur:
  - on-body injector for UDENYCA comes off before or during a dose delivery. Do not re-apply it.
  - on-body injector for UDENYCA is leaking.
  - adhesive on your on-body injector for UDENYCA becomes noticeably wet (saturated) with fluid, or there is dripping. This may mean that UDENYCA is leaking out of your on-body injector for UDENYCA. If this happens you may only receive some of your dose of UDENYCA, or you may not receive a dose at all.
  - on-body injector for UDENYCA status light is flashing red.

What is UDENYCA?
UDENYCA is a prescription medicine used to help reduce the chance of infection due to a low white blood cell count, in people with certain types of cancer (non-myeloid), who receive anti-cancer medicines (chemotherapy) that can cause fever and low blood cell count.

Do not take UDENYCA if you have had a serious allergic reaction to pegfilgrastim products or filgrastim products.

Before you receive UDENYCA, tell your healthcare provider about all of your medical conditions, including if you:

- have a sickle cell disorder.
- have had severe skin reactions to acrylic adhesives.
- have kidney problems.
- are pregnant or plan to become pregnant. It is not known if UDENYCA may harm your unborn baby.
- are breastfeeding or plan to breastfeed. It is not known if UDENYCA passes into your breast milk.

Tell your healthcare provider about all of the medicines you take, including prescription and over-the-counter medicines, vitamins, and herbal supplements.

How will I receive UDENYCA?
See the Instructions for Use for detailed information about how you will receive a dose of UDENYCA with the on-body injector for UDENYCA, and how to remove and dispose of the on-body injector for UDENYCA.

- See the section "What is the most important information I need to know about receiving UDENYCA with the on-body injector for UDENYCA?"
- UDENYCA is given as an injection under the skin (subcutaneous). Your healthcare provider will use a prefilled syringe with UDENYCA to fill the on-body injector prior to applying it. The prefilled syringe with UDENYCA and the on-body injector are provided to your healthcare provider as part of UDENYCA ONBODY. The on-body injector for UDENYCA will be applied to the stomach area (abdomen) or back of your arm by your healthcare provider. If the on-body injector for UDENYCA was placed on the back of your arm, a caregiver must be available to monitor the on-body injector for UDENYCA.
- Your healthcare provider should place the on-body injector for UDENYCA on an area of your skin that does not have swelling, redness, cuts, wounds, or abrasions. Tell your healthcare provider about any skin reactions that happen in the on-body injector for UDENYCA application area after it has been applied.
- The on-body injector for UDENYCA is programmed to deliver your dose about 27 hours after your healthcare provider places the on-body injector for UDENYCA on your skin.
- The dose of UDENYCA will be delivered over about 5 minutes. During dose delivery and for 1 hour after delivery, it is best to stay in a place where you or a caregiver can monitor the on-body injector for UDENYCA to make sure you receive your full dose of UDENYCA and watch for symptoms of an allergic reaction.
- Your healthcare provider will show you how to monitor the on-body injector for UDENYCA to make sure delivery has been completed.
- Keep the on-body injector for UDENYCA dry for about the last 3 hours before the dose delivery is expected to start. This will help you to better detect possible leaking from the on-body injector for UDENYCA.
- Only expose the on-body injector for UDENYCA to temperatures between 41°F to 104°F (5°C to 40°C).

While the on-body injector for UDENYCA is in place you should avoid:

- traveling, driving, or operating heavy machinery during hour 26 through hour 29 after the on-body injector for UDENYCA is applied.
- sleeping on the on-body injector for UDENYCA or applying pressure on the on-body injector for UDENYCA. The on-body injector for UDENYCA may not work properly.
- bumping the on-body injector for UDENYCA or knocking it off your body.
- using other materials to hold the on-body injector in place. Using other materials could cover audio or visual indicators or press the on-body injector against your skin, and lead to a missed dose or incomplete dose of UDENYCA.
- getting body lotion, creams, oils, and skin cleansing products near the on-body injector for UDENYCA. These products may loosen the adhesive that holds the on-body injector for UDENYCA onto your body.
- using bathtubs, hot tubs, whirlpools, or saunas, and direct sunlight. These may affect UDENYCA.
- peeling off or disturbing the on-body injector for UDENYCA adhesive before you receive your full dose of UDENYCA.

What are the possible side effects of UDENYCA?
UDENYCA may cause serious side effects, including:

- Spleen rupture. Your spleen may become enlarged and can rupture. A ruptured spleen can cause death. Call your healthcare provider right away if you have pain in your left upper stomach area or left shoulder.
- A serious lung problem called Acute Respiratory Distress Syndrome (ARDS). Call your healthcare provider or get emergency medical help right away if you have shortness of breath with or without a fever, trouble breathing, or a fast rate of breathing.
- Serious allergic reactions. UDENYCA can cause serious allergic reactions. These reactions can cause a rash over your whole body, shortness of breath, wheezing, dizziness, swelling around your mouth or eyes, fast heart rate, and sweating.
  If you have an allergic reaction during the delivery of UDENYCA, remove the on-body injector for UDENYCA by grabbing the edge of the adhesive pad and peeling off the on-body injector for UDENYCA. Get emergency medical help right away.
- Sickle cell crises. You may have a serious sickle cell crisis, which could lead to death, if you have a sickle cell disorder and receive UDENYCA. Call your healthcare provider right away if you develop symptoms of sickle cell crisis such as pain or difficulty breathing.
- Kidney injury (glomerulonephritis). UDENYCA can cause kidney injury. Call your healthcare provider right away if you develop any of the following symptoms:
  - swelling of your face or ankles
  - blood in your urine or dark colored urine
  - you urinate less than usual
- Increased white blood cell count (leukocytosis). Your healthcare provider will check your blood during treatment with UDENYCA.
- Decreased platelet count (thrombocytopenia). Your healthcare provider will check your blood during treatment with UDENYCA. Tell your healthcare provider if you have unusual bleeding or bruising during treatment with UDENYCA. This could be a sign of decreased platelet counts, which may reduce the ability of your blood to clot.
- Capillary Leak Syndrome. UDENYCA can cause fluid to leak from blood vessels into your body’s tissues. This condition is called “Capillary Leak Syndrome” (CLS). CLS can quickly cause you to have symptoms that may become life-threatening. Get emergency medical help right away if you develop any of the following symptoms:
  - swelling or puffiness and are urinating less than usual
  - trouble breathing
  - swelling of your stomach-area (abdomen) and feeling of fullness
  - dizziness or feeling faint
  - a general feeling of tiredness
- Myelodysplastic syndrome and acute myeloid leukemia. If you have breast cancer or lung cancer, when UDENYCA is used with chemotherapy and radiation therapy, or with radiation therapy alone, you may have an increased risk of developing a precancerous blood condition called myelodysplastic syndrome (MDS) or a blood cancer called acute myeloid leukemia (AML). Symptoms may include tiredness, fever, and easy bruising or bleeding. Call your healthcare provider if you develop these symptoms during treatment with UDENYCA.
- Inflammation of the aorta (aortitis). Inflammation of the aorta (the large blood vessel which transports blood from the heart to the body) has been reported in patients who received pegfilgrastim products. Symptoms may include fever, abdominal pain, feeling tired, and back pain. Call your healthcare provider if you experience these symptoms.

The most common side effect of UDENYCA is pain in your bones, and in your arms, and legs. These are not all the possible side effects of UDENYCA. For more information, ask your healthcare provider or pharmacist.
Call your doctor for medical advice about side effects. You may report side effects to FDA at 1-800-FDA-1088.

General information about the safe and effective use of UDENYCA.
Medicines are sometimes prescribed for purposes other than those listed in a Patient Information leaflet. If you would like more information about UDENYCA, talk with your healthcare provider or pharmacist. You can ask your pharmacist for information about UDENYCA that is written for health professionals.

What are the ingredients in UDENYCA?
Active ingredient: pegfilgrastim-cbqv
Inactive ingredients: acetate, polysorbate 20, sodium, and sorbitol in Water for Injection.

Manufactured by: Coherus BioSciences, Inc., Redwood City California 94065-1442
U.S. License No. 2023
©2021 Coherus BioSciences Inc. All rights reserved.
For more information go to www.UDENYCA.com, or call 1-800-4UDENYCA (1-800-483-3692)
PMD-0213, Rev.00

Coherus
BioSciences

This Patient Information has been approved by the U.S. Food and Drug Administration.

Issued: 12/2023

Healthcare Provider INSTRUCTIONS FOR USE
UDENYCA (yoo-den-i-kah) ONBODY™
(pegfilgrastim-cbqv)
injection, for subcutaneous use

Guide to Parts
UDENYCA Prefilled Syringe

On-body Injector for UDENYCA

Important
READ THE FOLLOWING INSTRUCTIONS BEFORE USING UDENYCA ONBODY
Prescribing Information

- See Prescribing Information for information on UDENYCA.
- The on-body injector is for adult patients only.
- The on-body injector is not recommended for patients with Hematopoietic Subsyndrome of Acute Radiation Syndrome.
- For patients who have had severe skin reactions to acrylic adhesives, consider the benefit-risk profile before administering pegfilgrastim via the on-body injector for UDENYCA.

Application Information

- The on-body injector should be applied to intact, non-irritated skin on the abdomen or back of the arm. The back of the arm may only be used if there is a caregiver available to monitor the status of the on-body injector.
- The on-body injector has a self-adhesive backing to attach it to the skin, do not use additional materials to hold it in place as this could lead to a missed or incomplete dose of UDENYCA.

Environmental Information

- Do not expose the on-body injector for UDENYCA to the following environments as the on-body injector may be damaged and the patient could be injured:
  - Diagnostic imaging (e.g., CT Scan, MRI, Ultrasound, X-ray)
  - Radiation treatment
  - Oxygen rich environments such as hyperbaric chambers.

Cautions

- Do not use UDENYCA ONBODY to deliver any other drug product.
- Do not use the on-body injector if its packaging has been previously opened, or the expiration date on the carton or any components has passed.
- Do not use if the name UDENYCA does not appear on UDENYCA ONBODY carton.
- Do not modify the on-body injector.
- Do not fill the UDENYCA on-body injector on the adhesive side. Use the metal medicine port.
- Do not attempt to reapply the on-body injector.
- Do not use if either the on-body injector or prefilled syringe is dropped. Start again with a new on-body injector or prefilled syringe.

Storage Information

- Store the ONBODY in the refrigerator at 36°F to 46°F (2°C to 8°C) until ready for use. If the ONBODY is stored at room temperature for more than 12 hours, do not use. Start again with a new ONBODY.
- Keep the prefilled syringe in the carton until use to protect from light.
- Do not freeze the ONBODY.
- Do not separate the components of UDENYCA ONBODY until ready for use.

For all questions, call Coherus BioSciences at 1-800-4UDENYCA (1-800-483-3692). If a patient calls you regarding any on-body injector problems, call Coherus BioSciences at 1 800-4UDENYCA (1-800-483-3692).

Step 1: Prepare
A| Remove ONBODY from the refrigerator and open carton.
Place the syringe tray and on-body injector tray on a clean, flat, well-lit work surface. Allow to come to room temperature for 30 minutes prior to use. Do not warm the UDENYCA ONBODY components using a heat source.
Check to make sure it contains:

- One UDENYCA prefilled syringe
- One on-body injector for UDENYCA
- UDENYCA Patient Information
- UDENYCA Prescribing Information
- Instructions for Use for healthcare provider
- Instructions for Use for patient

Check the above listed items for damage and check the expiry date on the syringe tray and on-body injector tray.
Do not use the on-body injector:

- if its packaging has been previously opened
- if the packaging or trays appear to be damaged or have been dropped
- if the expiry date on the syringe tray or on-body injector tray has passed.

B| Choose the patient’s injection site.
Choose the flattest site for the on-body injector application.
Ask the patient about their ability to monitor and remove the on-body injector.

- You can use the left or right side of the abdomen, except for a two-inch area right around navel.
- You can use the back of upper arm only if there is a caregiver available to monitor the status of the on-body injector.
- Apply the on-body injector to intact, non-irritated skin.
- Do not apply the on-body injector on areas with scar tissue, moles, or excessive hair. In case of excessive hair, carefully trim hair to get the on-body injector close to the skin.
- Do not apply the on-body injector on areas where belts, waistbands, or tight clothing may rub against, disturb, or dislodge the on-body injector.
- Do not apply the on-body injector on surgical sites.
- Do not apply the on-body injector on areas where the on-body injector will be affected by folds in the skin.

C| Clean an area on the injection site larger than the on-body injector adhesive backing.

- Thoroughly clean the site with alcohol to enhance on-body injector‘s adherence to the skin. Only use alcohol to clean the skin.
- Make sure the skin is oil-free prior to applying the on-body injector.
- Allow the skin to completely dry on its own (e.g. without blowing on or fanning the area) before attaching the on-body injector.
- Do not touch this area again before attaching the on-body injector.

Step 2: Get ready
A| Open on-body injector tray and remove plastic lid.

Wash your hands before use.
Open the on-body injector tray by fully removing the tray cover and removing the plastic lid.

- Do not remove the on-body injector from the tray before filling it.
- Do not remove the green fill guide.

B| Remove UDENYCA prefilled syringe from tray.
For safety reasons:

- Do not grasp the gray needle cap.
- Do not remove the gray needle cap until ready to fill the on-body injector.
- Do not grasp the plunger rod.

C| Inspect medicine and UDENYCA prefilled syringe. UDENYCA liquid should always be clear and colorless.

- Do not use if the liquid contains particulate matter or discoloration is observed prior to administration.
- Do not use if any part appears to be damaged, cracked or broken.
- Do not use if the gray needle cap is missing or not securely attached.
- Do not use if the expiration date printed on the label has passed.
- Do not remove the gray needle cap until ready to fill the on-body injector.
- Do not shake the prefilled syringe.

In all the above cases, start again with a new UDENYCA ONBODY. Call Coherus BioSciences at 1-800-4UDENYCA (1-800-483-3692).
D| Remove air bubbles in prefilled syringe. E| Orient the syringe with the needle facing downwards. Center the needle directly over the metal medicine port at a 90-degree angle. Insert the needle all the way into the port, avoiding sides.

Insert needle into metal medicine port at a 90-degree angle only.

- Do not fill the UDENYCA on-body injector on the adhesive side. Use the metal medicine port.
- Do not touch the plunger until the needle is fully inserted into the metal medicine port.
- Do not move the needle in the metal medicine port.
- Do not insert the needle more than once.
- Do not bend the needle. Avoid spilling the medicine.
- Do not remove the green fill guide before filling the on-body injector.

F| Fully depress the plunger rod to expel entire contents of the prefilled syringe into the on-body injector.

After filling completely, you will hear two beeps. The status light will start to flash green.
Remove the needle straight from the metal medicine port and dispose the empty syringe right away into a puncture proof container.

- Do not recap the needle.

G| Check to see if the on-body injector is full.

You should see the green status light flashing and a black line next to FULL on the fill indicator. If this is not the case, do not use.
Start again with a new UDENYCA ONBODY, and call Coherus BioSciences at 1-800-4UDENYCA (1-800-483-3692).

H| Remove on-body injector from tray, then firmly squeeze and lift the green fill guide away from the on-body injector. Dispose of green fill guide.
A drop of medicine may be visible
on the metal medicine port when the green fill
guide is removed.

Step 3: Apply
A| Peel away both pull tabs to show the adhesive. Never touch hands or gloves to the adhesive.
Make sure skin is dry prior to applying the on-body injector.

- Do not touch or contaminate the automatic needle opening.
- Do not pull off the adhesive pad or fold it.
- Do not place adhesive on skin that is damp.

In all cases, start again with a new UDENYCA ONBODY.
Call Coherus BioSciences at 1-800-4UDENYCA (1-800-483-3692).
B| Securely apply the on-body injector without folding and without wrinkling to the cleaned injection site so it is visible and can be monitored by the patient or caregiver.

- Do not touch the adhesive.
- Grasp the on-body injector’s plastic case with your fingertips and only by sides, keeping fingers off of the adhesive.
- Do not et the adhesive bend or curl while applying the on-body injector to skin.

Back of upper arm (triceps)
Vertical with the light facing down toward the elbow

Abdomen
Horizontal with the light facing up and visible to the patient

If the adhesive is wrinkled or has folds anywhere that prevent the on-body injector from securely adhering, remove the on-body injector. Start again with a new ONBODY and call Coherus BioSciences at 1-800-4UDENYCA (1-800-483-3692).

Step 4: Finish
A| Provide the Patient Instructions for Use Booklet for the patient to take home. Fill in the Dose Delivery information on the Patient Instructions for Use Booklet, and review the following instructions with your patient:

- The on-body injector will always flash a slow green light to let them know it is working properly.
- The patient should keep the on-body injector dry for at least 3 hours after it was placed on their skin.
- After approximately 27 hours the on-body injector will start to deliver the dose.
- Immediately before dose delivery starts the injection needle will be automatically inserted into the skin.
- When the dose delivery starts it will take about 5 minutes to complete. During this time, the on-body injector will flash a fast green light.
- When dose delivery is complete, the on-body injector will sound a long beep, and the status light will turn SOLID GREEN. The needle will retract automatically.
- Do not remove the on-body injector until the status light is SOLID GREEN.
- If the red error light is flashing, or the adhesive is noticeably wet (saturated), or the on-body injector is dislodged, the patient should contact their healthcare provider immediately as they may need a replacement dose.
- The patient should remain in a place where they can monitor the on-body injector for the entire dose delivery. The patient should avoid activities and settings that may interfere with wearing and monitoring during the dosing of UDENYCA administered by the on-body injector or could cause the OBI to fall off. For example, avoid traveling, driving, or operating heavy machinery during hours 26-29 following application of the on-body injector (this includes the approximately 5-minute delivery period plus an hour post-delivery).
- If the patient has an allergic reaction during the delivery of UDENYCA, the patient should remove the on-body injector and call his or her healthcare provider or seek emergency care right away.
- If placed on the back of the arm, remind the patient that a caregiver must be available to monitor the on-body injector.
- The on-body injector has a self-adhesive backing to attach it to the skin.
- Do not use other materials to hold it in place as this could cover audio/visual indicators or compress the on-body injector against the patient’s skin, as this could lead to a missed or incomplete dose of UDENYCA.
- Always dispose of the empty on-body injector in a sharps disposal container as instructed by your healthcare provider or by state or local laws.
- Keep the on-body injector at least four inches away from electrical equipment such as cell phones, cordless telephones, microwaves and other common appliances. Failure to keep the on-body injector at least this recommended distance may interfere with operation and can lead to a missed or incomplete dose of UDENYCA.

If at any time the on-body injector beeps continuously for five minutes, and the status light is flashing red, take the on-body injector off of the patient.

- Do not apply the on-body injector to the patient if red error light is on.
- Do not leave the on-body injector on the patient if red error light is on.

In all cases, do not use. Start over with a new UDENYCA ONBODY, and call 1-800-4UDENYCA (1-800-483-3692).
If the patient reports the red status light is on, they may not have received the full dose. Schedule a follow-up appointment and report the incident to Coherus BioSciences at 1-800-4UDENYCA (1-800-483-3692).
If the patient reports an on-body injector leak, they may not have received the full dose. Schedule a follow-up appointment and report the incident to Coherus BioSciences at 1-800-4UDENYCA (1-800-483-3692).

Manufactured by:
Coherus BioSciences, Inc.
Redwood City, CA 94065-1442
US License No. 2023
https://udenyca.com
1-800-4UDENYCA (1-800-483-3692)
Issued: 12/2023
PMD-0214 Rev. 00

Electromagnetic Compatibility

The delivery system is designed to conform to the electromagnetic compatibility (EMC) standard IEC 60601-1-2:2020 and to operate accurately in conjunction with other medical equipment which also meets the requirements of this standard under home and hospital use environments.

To avoid electromagnetic interference (EMI) that may affect the performance of the delivery system [(i) Dose accuracy, (ii) treatment duration, (iii) Injection Depth, (iv) Visual and audible feedback], do not use the delivery system near sources of strong electric and magnetic interference (EMI), such as MRI, ionizing radiation, CT, diathermy, electromagnetic security systems (e.g., metal detectors), and large electric motors. In addition, portable and mobile RF communication equipment, such as RF emitters, cellular telephones, 2- way radios, BluetoothTM devices, and microwave ovens in close proximity to this device may affect the operation of the delivery system. Some of these EMI sources (mostly RF emitters) may not be visible and the device can potentially be exposed to fields from these EMI sources without the user’s awareness.

If you identify or suspect that external RF sources or other equipment are influencing delivery system operation (from known or unknown sources), try to (as applicable) increase the delivery system distance from the EMI source.

Electromagnetic Emissions

The delivery system has been tested and found to comply with the limits for a Class B digital device, pursuant to Part 15 of the FCC rules. These limits are designed to provide reasonable protection against harmful interference in a residential installation.

If this delivery system does cause harmful interference to radio or television reception, which can be determined by turning the radio or television off and on, the user is encouraged to try to correct the interference by one or more of the following measures: Reorient or relocate the receiving antenna. Increase the separation between the equipment and receiver. Connect the radio or television to an outlet on a circuit different from that to which the receiver is connected. Consult the dealer or an experienced radio/TV technician.

Electromagnetic Immunity

The delivery system has been tested to comply in either a Home Healthcare Environment or Professional Healthcare Environment.

Proximity fields from RF wireless communications equipment Immunity

The delivery system is tested per IEC 61000-4-3 at Frequencies and Levels as specified below to ensure Enclosure Port Immunity to RF wireless communications equipment.

WARNING: Portable RF communications equipment (including peripherals such as antenna cables and external antennas) should be used no closer than 30 cm (12 inches) to any part of the Delivery System. Otherwise, degradation of the performance of this equipment could result.

WARNING: Use of this delivery system adjacent to other equipment should be avoided because it could result in improper operation. If such use is necessary, this equipment and the other equipment should be observed to verify that they are operating normally.

Symbols Glossary

Description

Symbol/Sub clause

Name or trade mark of the product

Part number

Name or trade name and address of the manufacturer

Serial number or batch code, preceded by the word 'LOT', or the serial number/NDC number;

Warnings and/or precautions to take (in text format)

Storage temperature and any other special storage and/or handling conditions (for the combination)

Humidity limitation (for the combination)

Pressure limitation (for the combination)

Do not use if package is damaged

Keep away from sunlight

Keep dry

For electrical devices - Water and dust ingress rating

For electrical devices – refer to instruction for use

"Rx only" labeling of prescription devices

Sterile & Sterilization by EO

Expiration date (Use by)

The device is for single use

Should not enter the MRI scanner room

Type BF applied parts

CSA Certificate

Battery specification Li-MnO2 Battery 3V/850mAH (CR14250)

N/A

WEEE directive compliance

UDENYCA® (pegfilgrastim-cbqv) prefilled syringe

On-body injector for UDENYCA® (pegfilgrastim-cbqv)

Patient INSTRUCTIONS FOR USE
UDENYCA (yoo-den-i-kah) ONBODY™
(pegfilgrastim-cbqv)
injection, for subcutaneous use

Dose Delivery Information

Get to Know Your On-body Injector

Flashing Green: The on-body injector is working properly. Do not remove the on-body injector if the status light is flashing green.
Solid Green (or off): Signals dose delivery is complete. Check to see if fill indicator reads empty.
Flashing Red: On-body injector error. If you hear beeping at any time, check the status light. If it is flashing red, call your healthcare provider right away as you may need a replacement dose.
Fill indicator: Black line shows how much UDENYCA is in the on-body injector.

Important Information
On-body Injector for UDENYCA Description

- The on-body injector for UDENYCA is intended for delivery of UDENYCA. This on-body injector delivers UDENYCA with an injection under-the-skin (subcutaneous). See the Patient Information that comes with your on-body injector for important information.
- Your healthcare provider will use a prefilled syringe with UDENYCA to fill the on-body injector prior to applying it. The prefilled syringe with UDENYCA and the on-body injector are provided to your healthcare provider as part of UDENYCA ONBODY. The on-body injector is applied directly to your skin using a self- adhesive backing. The on-body injector lets you know its status with sounds and lights.

Warnings

- You should only receive a dose of UDENYCA on the day your healthcare provider tells you.
- You should not receive your dose of UDENYCA any sooner than 24 hours after you finish receiving your chemotherapy. The on-body injector for UDENYCA is programmed to deliver your dose about 27 hours after your healthcare provider places the on-body injector on your skin.
- If you have concerns about your medicine, call your healthcare provider right away. Serious allergic reactions can happen with UDENYCA. Ask your caregiver to be nearby for the first use. Plan to be in a place where you or your caregiver can closely monitor the on-body injector for UDENYCA for about 5-minutes during UDENYCA delivery and for an hour after the delivery.
- Do not take UDENYCA if you have had a serious allergic reaction to pegfilgrastim products or to filgrastim products.
- Tell your healthcare provider if you have had severe skin reactions to acrylic adhesives.
- If you have an allergic reaction during the delivery of UDENYCA, remove the on- body injector by grabbing the edge of the adhesive pad and peeling off the on- body injector. Get emergency medical help right away. Caution the needle may be exposed. Dispose of the on-body injector into a sharps disposal container right away.
- Call your healthcare provider right away if you have severe pain or skin discomfort around your on-body injector.
- Call your healthcare provider right away if you have pain in your left upper stomach area or left shoulder area. This pain could mean your spleen is enlarged or ruptured.
- Call your healthcare provider or get emergency medical help right away if you get any of these symptoms of acute respiratory distress syndrome (ARDS): fever, shortness of breath, trouble breathing, or a fast rate of breathing.
- Call your healthcare provider right away if you experience any of these symptoms of kidney injury (glomerulonephritis): puffiness in your face or ankles, blood in your urine or brown colored urine or you notice you urinate less than usual.
- Call your healthcare provider if you have persistent or worsening redness or tenderness at the application site (may be a sign of infection).
- The on-body injector is for adult patients only.

Wearing the On-body Injector

- This on-body injector delivers UDENYCA with an under-the-skin (subcutaneous) injection.
- The on-body injector is small, for one-time use, lightweight, battery-powered, and waterproof up to 5 feet (1.5 meters) for 1 hour.
- The on-body injector can be worn in a shower. After showering, check the on- body injector to make sure it has not become loose (dislodged).
- Avoid getting body lotions, creams, oils or cleaning agents near the on-body injector as these products may loosen the adhesive. Before your next scheduled UDENYCA dose, avoid use of lotions, creams, or oils on your arms and stomach area (abdomen).
- Only expose the on-body injector to temperatures between 41°F and 104°F (5°C and 40°C).
- Do not use bathtubs, hot tubs, whirlpools, or saunas while wearing the on-body injector. This may affect your medicine.
- Do not expose the on-body injector to direct sunlight. If the on-body injector is exposed to direct sunlight for more than 1 hour, it may affect your medicine. Wear the on-body injector under clothing.
- Do not sleep on the on-body injector or apply pressure during wear, especially during dose delivery. This may affect on-body injector performance.
- Do not peel off or disturb the on-body injector adhesive before your full dose is complete. This may result in a missed or incomplete dose of UDENYCA.

Environmental Precautions

- Do not expose the on-body injector to the following because the on-body injector may be damaged and you could be injured:
  - Diagnostic imaging (e.g., CT Scan, MRI, Ultrasound, X-ray)
  - Radiation treatment
  - Oxygen rich environments, such as hyperbaric chambers.
- Keep the on-body injector at least 4 inches away from electrical equipment such as cell phones, cordless telephones, microwaves and other common appliances. Failure to keep the on-body injector at least this recommended distance may interfere with operation and can lead to a missed or incomplete dose of UDENYCA.
- Avoid activities and places that may interfere with monitoring during the dosing of UDENYCA administered by the on-body injector. For example, avoid traveling, driving, or operating heavy machinery during hours 26-29 following application of the on-body injector for UDENYCA (this includes the 5-minute dose delivery period plus an hour post-delivery).
- If you must travel by airplane before the approximately 5-minute dose delivery period with the on-body injector, avoid airport X-ray scans. Request a manual pat down instead. Use care during a manual pat down to help prevent the on-body injector from being accidentally removed. For more information go to: http://www.tsa.gov/travelerinformation/travelers-disabilities-and-medical-conditions

A healthcare provider who is familiar with UDENYCA should answer your questions. For general questions or support call 1-800-4UDENYCA (1-800-483-3692) or visit www.udenyca.com.

Step 1: Monitor On-body Injector
A| For the next 27 hours, occasionally check the status light for at least 10 seconds. If the status light is flashing green, it is okay.

- Keep the on-body injector and adhesive backing dry for at least 3 hours after it was placed on your skin, and for 3 hours prior to dose delivery.
- Be careful not to bump the on-body injector, or knock the on-body injector off your body.
- The on-body injector has a self-adhesive backing to attach it to the skin. Do not add other materials to hold it in place as this could lead to a missed or incomplete dose of UDENYCA.

- If the on-body injector was placed on the back of your arm, a caregiver must be available to monitor the status of the on-body injector.
- If the on-body injector comes away from your skin at any time, do not reapply it. Call your healthcare provider right away as you may need a replacement dose. Caution the needle may be exposed. Dispose of the on-body injector into a sharps disposal container right away.
- If you hear beeping at any time, check the status light. If it is flashing red, call your healthcare provider right away, as you may need a replacement dose.

Step 2: Observe Dose Delivery
A| After about 27 hours, your on-body injector will begin to deliver your dose of UDENYCA.

- Right before the injection starts the injection needle will be automatically inserted into the skin.
- Dose delivery will take around 5-minutes to complete. The on-body injector will flash a fast, green light.
- You may hear the pump working. This is okay.

- When dose delivery is complete, a long beep will sound and the status light will turn solid green.
- If you hear beeping at any time, check the status light. If it is flashing red, call your healthcare provider right away, as you may need a replacement dose.

- If the adhesive is noticeably wet or dripping with medicine, call your healthcare provider right away, as you may need a replacement dose.

Step 3: Verify Dose Complete
A| After the beep, check the color of the status light. B| Grab the edge of the adhesive pad. Slowly peel off the on-body injector.

- Do not grasp the on-body injector itself to try to pull it off of your body.
- If medicine has leaked or the adhesive is noticeably wet or dripping, call your healthcare provider right away, as you may not have received your full dose and you may need a replacement dose.
- Remove any extra adhesive using soap and water.

Step 4: Finish

- Check your status light. Watch for at least 10 seconds. If the status light is solid green or it has switched off, it is okay.
- You should see a black line next to the EMPTY indicator. If the on-body injector is not empty, call your healthcare provider right away, as you may need a replacement dose.

- If you hear beeping, or when you check the status light and it is flashing red, call your healthcare provider right away.
- If the needle is exposed, call your healthcare provider right away.

A| Check off the box below to record how your on-body injector looks after use. B| Properly dispose of the on-body injector.

- After on-body injector removal, place the on-body injector in a sharps disposal container whether the needle is exposed or not.
- The on-body injector contains batteries, electronics, and a needle. Put the on-body injector in a FDA-cleared sharps disposal container right away after use. Do not throw away (dispose of) the on-body injector in your household trash.
- If you do not have a FDA-cleared sharps disposal container, you may use a household container that is:
  - made of a heavy-duty plastic,
  - can be closed with a tight-fitting, puncture-resistant lid, without sharps being able to come out,
  - upright and stable during use,
  - leak-resistant, and
  - properly labeled to warn of hazardous waste inside the container.
- When your sharps disposal container is almost full, you will need to follow your community guidelines for the right way to dispose of your sharps disposal container. There may be state or local laws about how you should throw away used needles and syringes.

- Do not dispose of your used sharps disposal container in your household trash unless your community guidelines permit this. Do not recycle your used sharps disposal container.
- For more information about safe sharps disposal, and for specific information about sharps disposal in the state that you live in, go to FDA's website at: http://www.fda.gov/safesharpsdisposal.
- Keep the used on-body injector and sharps disposal container away from children.

Frequently Asked Questions
How do I know it is safe to remove the on-body injector? It is safe to remove the on-body injector after checking the following:

- The status light should be solid green.
- If the status light is flashing green, the dose delivery is not complete. Wait until you hear a long beep and the status light turns solid green before removing your on-body injector.
- The status light turns off 1 hour after delivery completion.
- The fill indicator should have a black line next to EMPTY.

- If the status light is flashing red, you may not have received your full dose and may need a replacement dose. Call your healthcare provider right away.

Call your healthcare provider right away if the on-body injector at any time comes away from your skin before your full dose delivery, as you may need a replacement dose.
Do not reapply it. Caution the needle may be exposed. Dispose of the on-body injector into a sharps disposal container right away. If there is blood, press a clean cotton ball or gauze pad on the application site. Apply an adhesive bandage if needed. Call your healthcare provider right away if you experience persistent or worsening redness or tenderness at the application site, as this can be a sign of infection.

Manufactured by:
Coherus BioSciences, Inc.
Redwood City, CA 94065-1442
US License No. 2023
https://udenyca.com
1-800-4UDENYCA (1-800-483-3692)
Issued: 12/2023
PMD-0215 Rev. 00

Electromagnetic Compatibility

The delivery system is designed to conform to the electromagnetic compatibility (EMC) standard IEC 60601-1-2:2020 and to operate accurately in conjunction with other medical equipment which also meets the requirements of this standard under home and hospital use environments.

To avoid electromagnetic interference (EMI) that may affect the performance of the delivery system [(i) Dose accuracy, (ii) treatment duration, (iii) Injection Depth, (iv) Visual and audible feedback], do not use the delivery system near sources of strong electric and magnetic interference (EMI), such as MRI, ionizing radiation, CT, diathermy, electromagnetic security systems (e.g., metal detectors), and large electric motors. In addition, portable and mobile RF communication equipment, such as RF emitters, cellular telephones, 2- way radios, BluetoothTM devices, and microwave ovens in close proximity to this device may affect the operation of the delivery system. Some of these EMI sources (mostly RF emitters) may not be visible and the device can potentially be exposed to fields from these EMI sources without the user’s awareness.

If you identify or suspect that external RF sources or other equipment are influencing delivery system operation (from known or unknown sources), try to (as applicable) increase the delivery system distance from the EMI source.

Electromagnetic Emissions

The delivery system has been tested and found to comply with the limits for a Class B digital device, pursuant to Part 15 of the FCC rules. These limits are designed to provide reasonable protection against harmful interference in a residential installation.

If this delivery system does cause harmful interference to radio or television reception, which can be determined by turning the radio or television off and on, the user is encouraged to try to correct the interference by one or more of the following measures: Reorient or relocate the receiving antenna. Increase the separation between the equipment and receiver. Connect the radio or television to an outlet on a circuit different from that to which the receiver is connected. Consult the dealer or an experienced radio/TV technician.

Electromagnetic Immunity

The delivery system has been tested to comply in either a Home Healthcare Environment or Professional Healthcare Environment.

Proximity fields from RF wireless communications equipment Immunity

The delivery system is tested per IEC 61000-4-3 at Frequencies and Levels as specified below to ensure Enclosure Port Immunity to RF wireless communications equipment.

WARNING: Portable RF communications equipment (including peripherals such as antenna cables and external antennas) should be used no closer than 30 cm (12 inches) to any part of the Delivery System. Otherwise, degradation of the performance of this equipment could result.

WARNING: Use of this delivery system adjacent to other equipment should be avoided because it could result in improper operation. If such use is necessary, this equipment and the other equipment should be observed to verify that they are operating normally.

Symbols Glossary

Description

Symbol/Sub clause

Name or trade mark of the product

Part number

Name or trade name and address of the manufacturer

Serial number or batch code, preceded by the word ‘LOT’, or the serial number/NDC number;

Warnings and/or precautions to take (in text format)

Storage temperature and any other special storage and/or handling conditions (for the combination)

Humidity limitation (for the combination)

Pressure limitation (for the combination)

Do not use if package is damaged

Keep away from sunlight

Keep dry

For electrical devices - Water and dust ingress rating

For electrical devices – refer to instruction for use

"Rx only" labeling of prescription devices

Sterile & Sterilization by EO

Expiration date (Use by)

The device is for single use

Should not enter the MRI scanner room

Type BF applied parts

CSA Certificate

Battery specification Li-MnO2 Battery 3V/850mAH (CR14250)

N/A

WEEE directive compliance

UDENYCA® (pegfilgrastim-cbqv) prefilled syringe

On-body injector for UDENYCA® (pegfilgrastim-cbqv)

PACKAGE LABEL

Carton Label - One 6 mg/0.6 mL Single-Dose Prefilled Syringe - UDENYCA

PRINCIPAL DISPLAY PANEL

Coherus
BioSciences

6 mg/
0.6 mL

NDC 70114-101-01

UDENYCA®
pegfilgrastim-cbqv
Injection

Rx Only

6 mg in 0.6 mL Single-Dose Prefilled
Syringe
For Subcutaneous Use
Sterile Solution - No Preservative

Pegylated Recombinant
Methionyl Human Granulocyte
Colony-Stimulating Factor
(PEG-r-metHuG-CSF) derived
from E. coli

One 6 mg/0.6 mL single-dose
Prefilled Syringe

PACKAGE LABEL

Carton Label - One 6 mg/0.6 mL Single-Dose Prefilled AUTOINJECTOR - UDENYCA

PRINCIPAL DISPLAY PANEL

NDC 70114-120-01

UDENYCA®
pegfilgrastim-cbqv
Injection

Rx Only

6 mg in 0.6 mL Single-Dose Prefilled AUTOINJECTOR
For Subcutaneous Use Sterile Solution - No Preservative

One 6 mg/0.6 mL Single-Dose Prefilled Autoinjector

Pegylated Recombinant Methionyl Human
Granulocyte Colony-Stimulating Factor
(PEG-r-metHuG-CSF) derived from E. coli

Coherus™

6 mg/0.6 mL

PACKAGE LABEL

Carton Label - One 6 mg/0.6 mL Single-Dose Prefilled On-body Injector (OBI) - UDENYCA

PRINCIPAL DISPLAY PANEL

Coherus®

6 mg/
0.6 mL*

See package insert for full
Prescribing Information
and Instructions for Use.

Rx
Only

1 - Single-Dose UDENYCA Prefilled Syringe
1 - Sterile On-body Injector for UDENYCA

NDC 70114-130-01

UDENYCA® ONBODY™
(pegfilgrastim-cbqv)

Injection

Pegylated Recombinant Methionyl Human Granulocyte
Colony-Stimulating Factor (PEG-r-metHuG-CSF) derived from E. Coli

*Prefilled syringe contains 0.67 mL to deliver 6 mg/0.6 mL
when used with On-bodv Injector.

For Subcutaneous Use Only

Carton Contents (intended to be dispensed as a unit):

- 1 Sterile On-body Injector for UDENYCA
- 1 UDENYCA Prefilled Syringe Labeled for Use With
  On-body Injector Only
- 1 Prescribing Information and 1 Patient information
- 1 Patient Instructions for Use
- 1 Healthcare Provider Instructions for Use

- Store refrigerated at 2°C to 8°C
  (36°F to 46°F)
- Keep in carton to protect from light
- Do not freeze. Do not shake